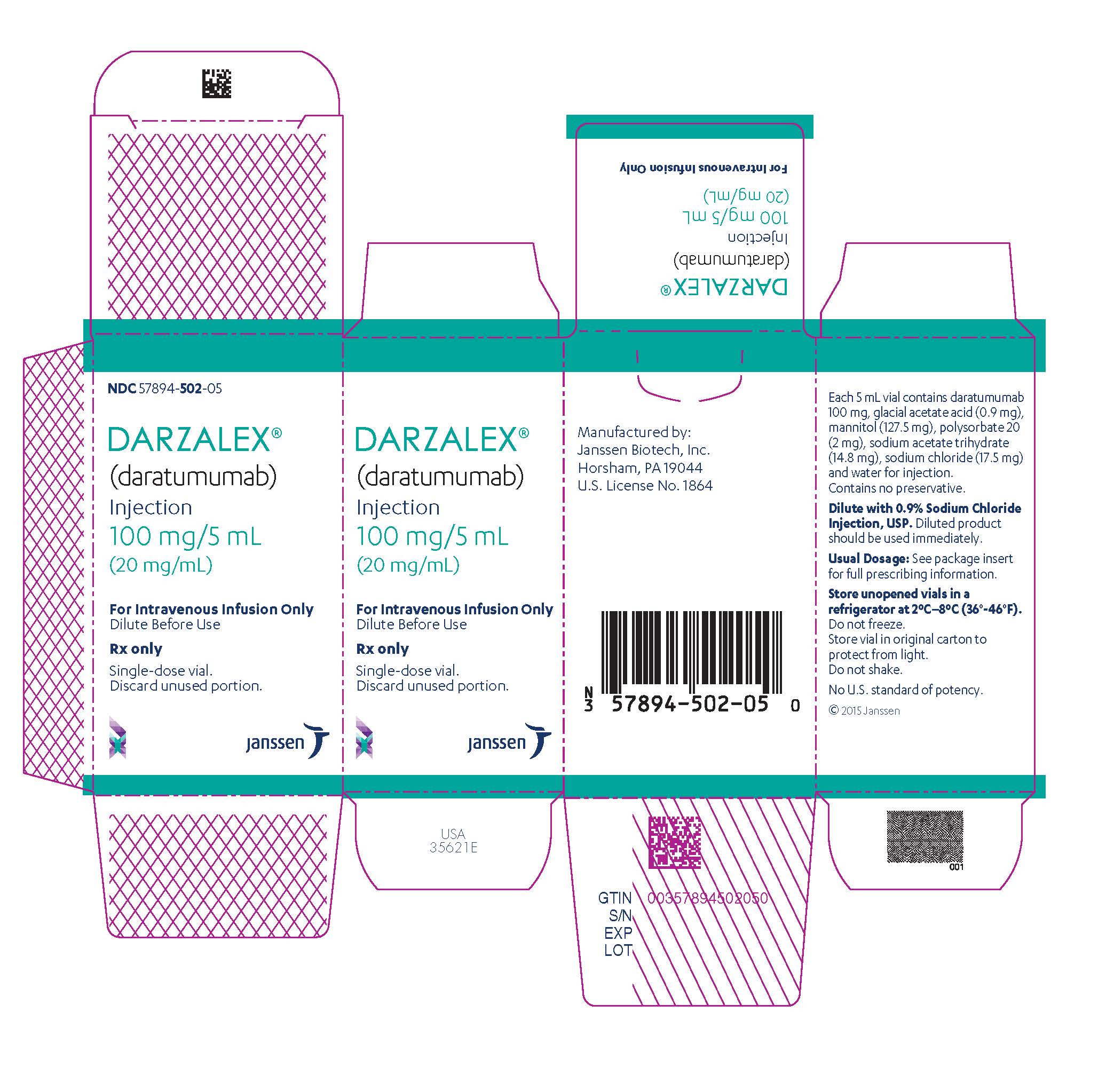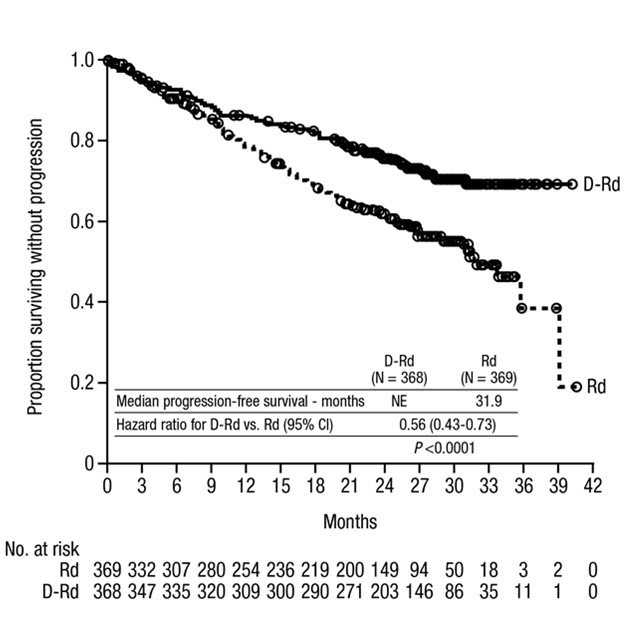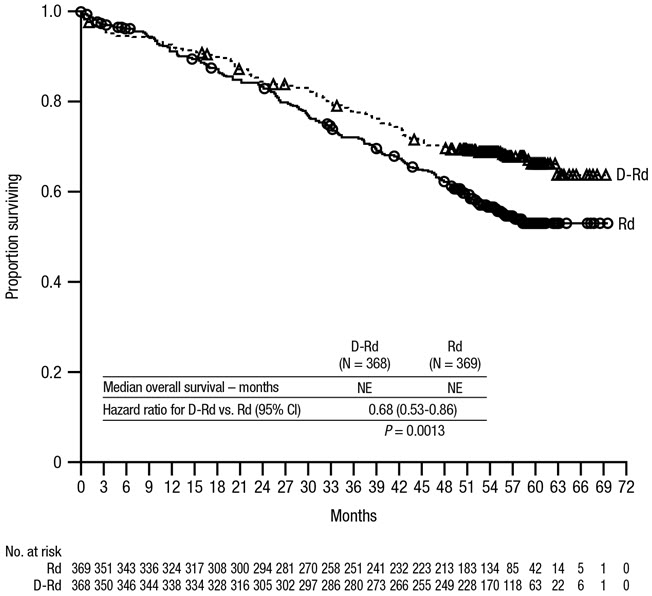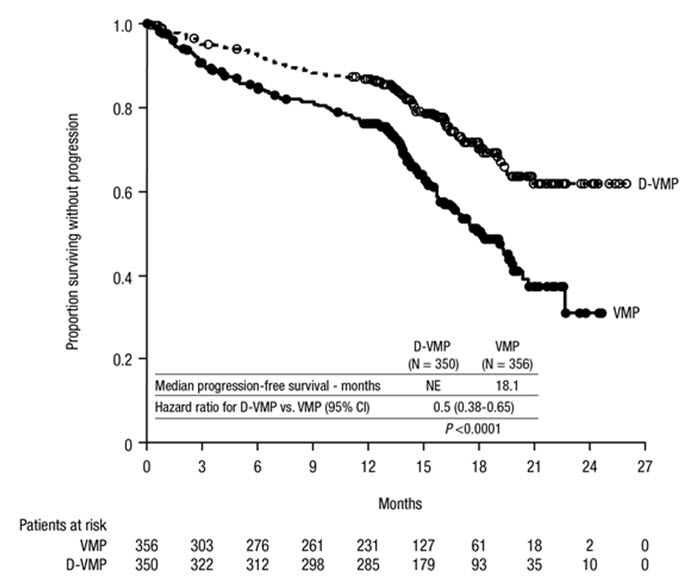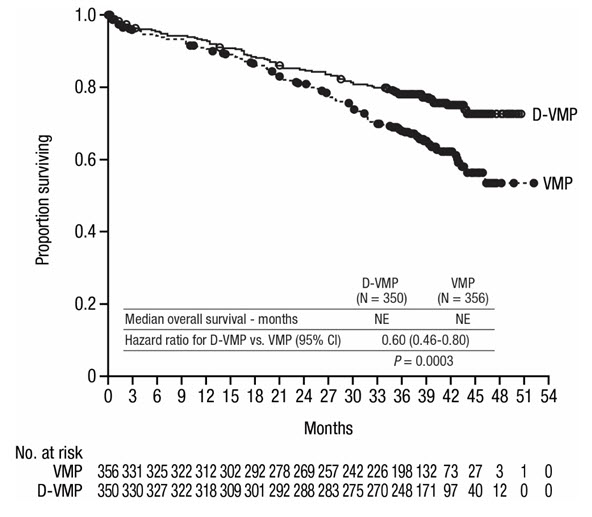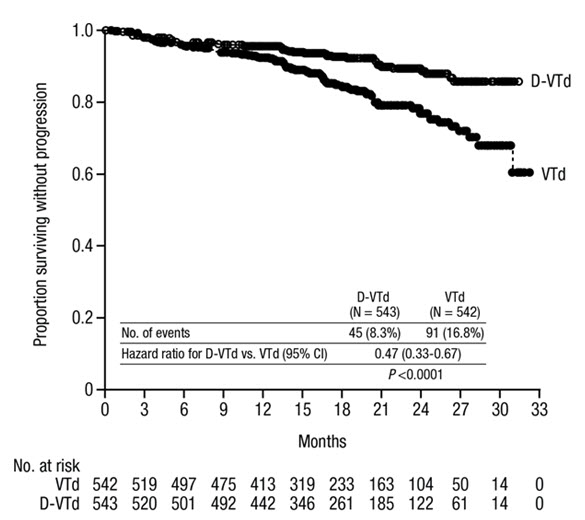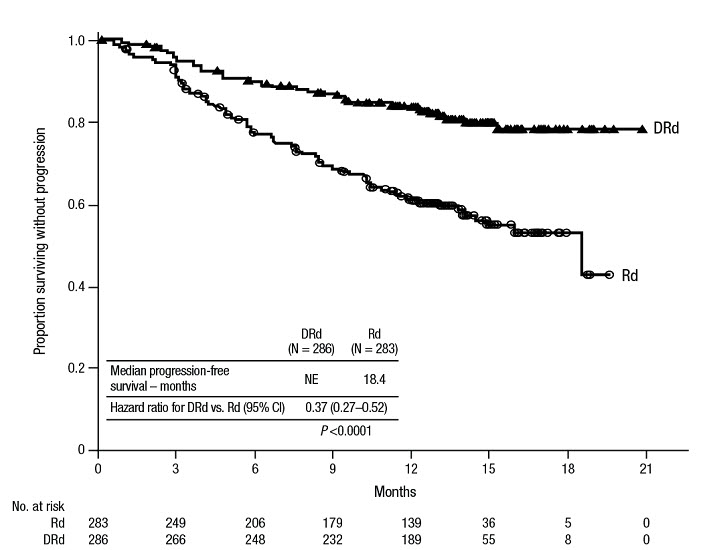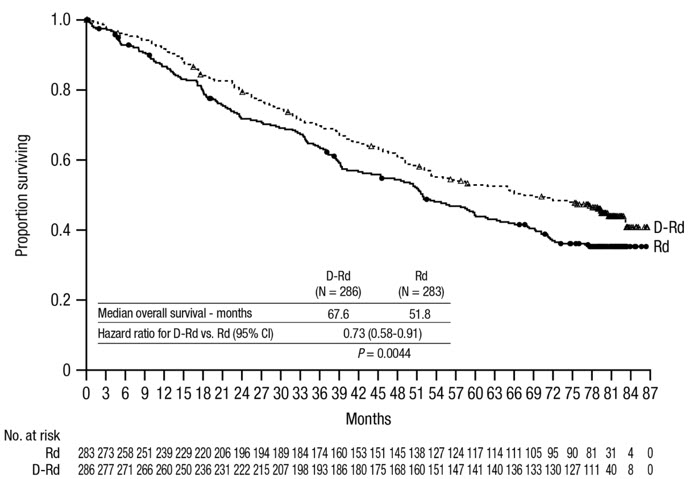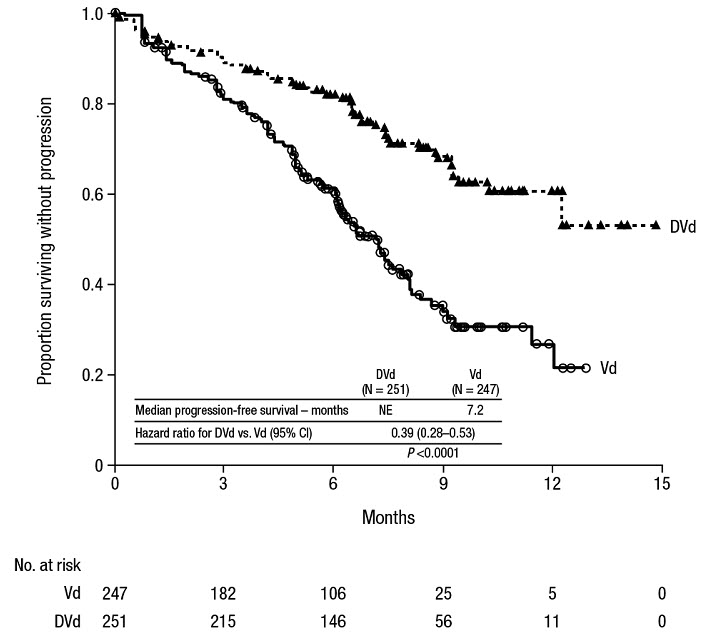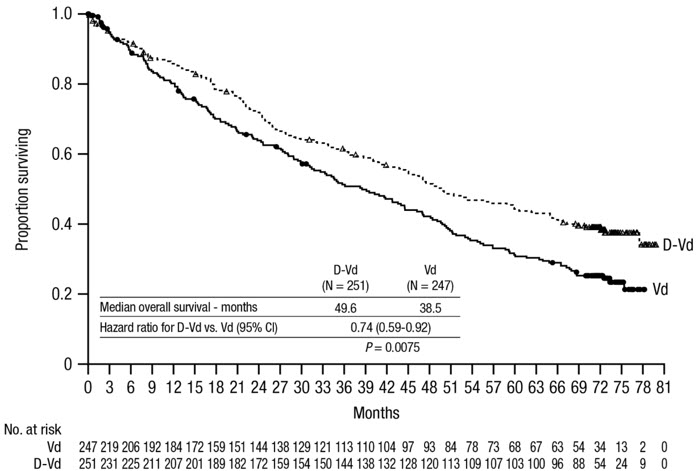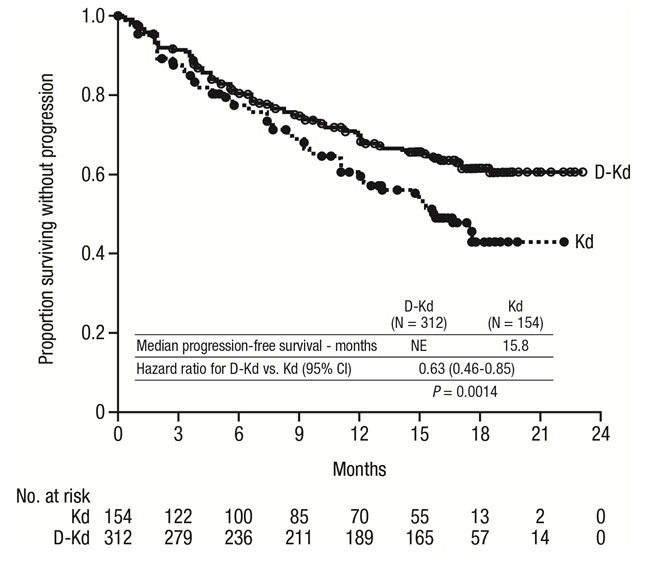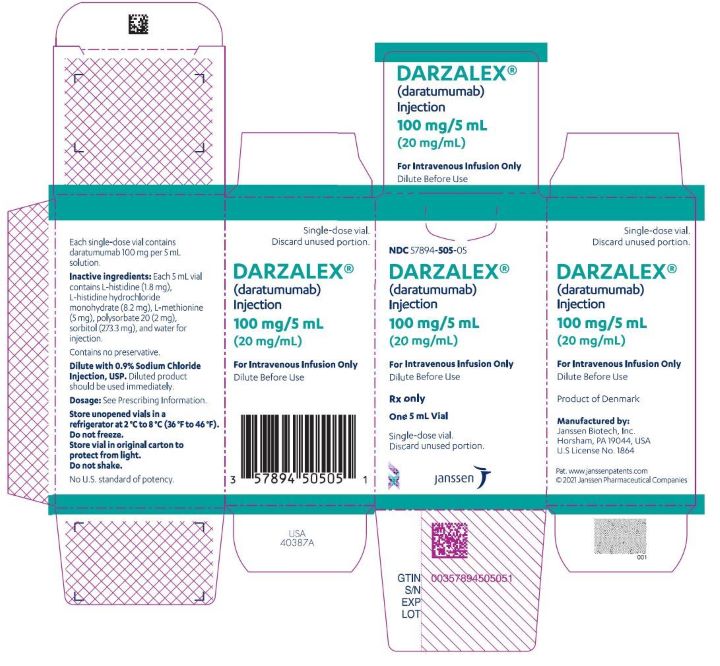 DRUG LABEL: DARZALEX
NDC: 57894-502 | Form: INJECTION, SOLUTION, CONCENTRATE
Manufacturer: Janssen Biotech, Inc.
Category: prescription | Type: HUMAN PRESCRIPTION DRUG LABEL
Date: 20251117

ACTIVE INGREDIENTS: DARATUMUMAB 100 mg/5 mL
INACTIVE INGREDIENTS: ACETIC ACID; SODIUM ACETATE; SODIUM CHLORIDE; MANNITOL; POLYSORBATE 20; WATER

HIGHLIGHTS OF PRESCRIBING INFORMATION

These highlights do not include all the information needed to use DARZALEX safely and effectively. See full prescribing information for DARZALEX.
DARZALEX®(daratumumab) injection, for intravenous use
Initial U.S. Approval: 2015

1 INDICATIONS AND USAGE

DARZALEX is a CD38-directed cytolytic antibody indicated for the treatment of adult patients with multiple myeloma:

- in combination with lenalidomide and dexamethasone in newly diagnosed patients who are ineligible for autologous stem cell transplant and in patients with relapsed or refractory multiple myeloma who have received at least one prior therapy
- in combination with bortezomib, melphalan and prednisone in newly diagnosed patients who are ineligible for autologous stem cell transplant
- in combination with bortezomib, thalidomide, and dexamethasone in newly diagnosed patients who are eligible for autologous stem cell transplant
- in combination with bortezomib and dexamethasone in patients who have received at least one prior therapy
- in combination with carfilzomib and dexamethasone in patients with relapsed or refractory multiple myeloma who have received one to three prior lines of therapy
- in combination with pomalidomide and dexamethasone in patients who have received at least two prior therapies including lenalidomide and a proteasome inhibitor
- as monotherapy, in patients who have received at least three prior lines of therapy including a proteasome inhibitor (PI) and an immunomodulatory agent or who are double-refractory to a PI and an immunomodulatory agent. (1)

2 DOSAGE AND ADMINISTRATION

- Pre-medicate with corticosteroids, antipyretics and antihistamines. (2.3)
- Dilute and administer as an intravenous infusion. (2.5)
- Recommended dose is 16 mg/kg actual body weight. See full prescribing information for drugs used in combination and schedule. (2.2)
- Administer post-infusion medications. (2.3)

3 DOSAGE FORMS AND STRENGTHS

Injection:

- 100 mg/5 mL (20 mg/mL) solution in a single-dose vial (3)
- 400 mg/20 mL (20 mg/mL) solution in a single-dose vial (3)

4 CONTRAINDICATIONS

Patients with a history of severe hypersensitivity to daratumumab or any of the components of the formulation. (4)

5 WARNINGS AND PRECAUTIONS

- Infusion-related reactions: Interrupt DARZALEX infusion for infusion-related reactions of any severity. Permanently discontinue the infusion in case of anaphylactic reactions or life-threatening infusion-related reactions and institute appropriate emergency care. (2.4, 5.1)
- Interference with cross-matching and red blood cell antibody screening: Type and screen patients prior to starting treatment. Inform blood banks that a patient has received DARZALEX. (5.2, 7.1)
- Neutropenia: Monitor complete blood cell counts periodically during treatment. Monitor patients with neutropenia for signs of infection. Dose delay may be required to allow recovery of neutrophils. (5.3)
- Thrombocytopenia: Monitor complete blood cell counts periodically during treatment. Dose delay may be required to allow recovery of platelets. (5.4)
- Embryo-Fetal Toxicity: Can cause fetal harm. Advise pregnant women of the potential risk to a fetus and advise females of reproductive potential to use effective contraception. (5.6, 8.1, 8.3)

6 ADVERSE REACTIONS

The most frequently reported adverse reactions (incidence ≥20%) are: upper respiratory infection, neutropenia, infusion-related reactions, thrombocytopenia, diarrhea, constipation, anemia, peripheral sensory neuropathy, fatigue, peripheral edema, nausea, cough, pyrexia, dyspnea, and asthenia. (6.1)

To report SUSPECTED ADVERSE REACTIONS, contact Janssen Biotech, Inc. at 1-800-526-7736 (1-800-JANSSEN) or FDA at 1-800-FDA-1088 or www.fda.gov/medwatch.

FULL PRESCRIBING INFORMATION

1 INDICATIONS AND USAGE

DARZALEX is indicated for the treatment of adult patients with multiple myeloma:

- in combination with lenalidomide and dexamethasone in newly diagnosed patients who are ineligible for autologous stem cell transplant and in patients with relapsed or refractory multiple myeloma who have received at least one prior therapy.
- in combination with bortezomib, melphalan and prednisone in newly diagnosed patients who are ineligible for autologous stem cell transplant.
- in combination with bortezomib, thalidomide, and dexamethasone in newly diagnosed patients who are eligible for autologous stem cell transplant.
- in combination with bortezomib and dexamethasone in patients who have received at least one prior therapy.
- in combination with carfilzomib and dexamethasone in patients with relapsed or refractory multiple myeloma who have received one to three prior lines of therapy.
- in combination with pomalidomide and dexamethasone in patients who have received at least two prior therapies including lenalidomide and a proteasome inhibitor.
- as monotherapy, in patients who have received at least three prior lines of therapy including a proteasome inhibitor (PI) and an immunomodulatory agent or who are double-refractory to a PI and an immunomodulatory agent.

2 DOSAGE AND ADMINISTRATION

2.1 Important Dosing Information

- Administer pre-infusion and post-infusion medications [see Dosage and Administration (2.3)] .
- Administer only as an intravenous infusion after dilution in 0.9% Sodium Chloride Injection [see Dosage and Administration (2.5)].
- DARZALEX should be administered by a healthcare provider, with immediate access to emergency equipment and appropriate medical support to manage infusion-related reactions if they occur [see Warnings and Precautions (5.1)].
- Type and screen patients prior to starting DARZALEX [see Warnings and Precautions (5.2)] .

2.2 Recommended Dosage

Monotherapy and In Combination with Lenalidomide (D-Rd) or Pomalidomide (D-Pd) and Dexamethasone

The DARZALEX dosing schedule in Table 1 is for combination therapy (4-week cycle regimens) and monotherapy as follows:

- combination therapy with lenalidomide and low-dose dexamethasone for newly diagnosed patients ineligible for autologous stem cell transplant (ASCT) and in patients with relapsed/refractory multiple myeloma

- combination therapy with pomalidomide and low-dose dexamethasone for patients with relapsed/refractory multiple myeloma

- monotherapy for patients with relapsed/refractory multiple myeloma.

The recommended dose of DARZALEX is 16 mg/kg actual body weight administered as an intravenous infusion according to the following dosing schedule:

Table 1: DARZALEX Dosing Schedule in Combination With Lenalidomide or Pomalidomide (4-Week Cycle) and Low-Dose Dexamethasone and for Monotherapy
Weeks | Schedule
Weeks 1 to 8 | weekly (total of 8 doses)
Weeks 9 to 24 [First dose of the every-2-week dosing schedule is given at Week 9] | every two weeks (total of 8 doses)
Week 25 onwards until disease progression [First dose of the every-4-week dosing schedule is given at Week 25] | every four weeks

For dosing instructions of combination agents administered with DARZALEX, see Clinical Studies (14)and manufacturer's prescribing information.

In Combination with Bortezomib, Melphalan and Prednisone (D-VMP)

The DARZALEX dosing schedule in Table 2 is for combination therapy with bortezomib, melphalan and prednisone (6-week cycle regimen) for patients with newly diagnosed multiple myeloma ineligible for ASCT.

The recommended dose of DARZALEX is 16 mg/kg actual body weight administered as an intravenous infusion according to the following dosing schedule:

Table 2: DARZALEX Dosing Schedule in Combination With Bortezomib, Melphalan and Prednisone ([VMP], 6-Week Cycle)
Weeks | Schedule
Weeks 1 to 6 | weekly (total of 6 doses)
Weeks 7 to 54 [First dose of the every-3-week dosing schedule is given at Week 7] | every three weeks (total of 16 doses)
Week 55 onwards until disease progression [First dose of the every-4-week dosing schedule is given at Week 55] | every four weeks

For dosing instructions of combination agents administered with DARZALEX see Clinical Studies (14.1).

In Combination with Bortezomib, Thalidomide and Dexamethasone (D-VTd)

The DARZALEX dosing schedule in Table 3 is for combination therapy with bortezomib, thalidomide, and dexamethasone (4-week cycle regimen) for patients with newly diagnosed multiple myeloma eligible for ASCT.

The recommended dose of DARZALEX is 16 mg/kg actual body weight administered as an intravenous infusion according to the following dosing schedule:

Table 3: DARZALEX Dosing Schedule in Combination With Bortezomib, Thalidomide and Dexamethasone ([VTd]; 4-Week Cycle)
Treatment phase | Weeks | Schedule
Induction | Weeks 1 to 8 | weekly (total of 8 doses)
Induction | Weeks 9 to 16 [First dose of the every-2-week dosing schedule is given at Week 9] | every two weeks (total of 4 doses)
Stop for high dose chemotherapy and ASCT
Consolidation | Weeks 1 to 8 [First dose of the every-2-week dosing schedule is given at Week 1 upon re-initiation of treatment following ASCT] | every two weeks (total of 4 doses)

For dosing instructions of combination agents administered with DARZALEX, see Clinical Studies (14.1)and the manufacturer's prescribing information.

In Combination with Bortezomib and Dexamethasone (D-Vd)

The DARZALEX dosing schedule in Table 4 is for combination therapy with bortezomib and dexamethasone (3-week cycle) for patients with relapsed/refractory multiple myeloma.

The recommended dose of DARZALEX is 16 mg/kg actual body weight administered as an intravenous infusion according to the following dosing schedule:

Table 4: DARZALEX Dosing Schedule With Bortezomib and Dexamethasone (3-Week Cycle)
Weeks | Schedule
Weeks 1 to 9 | weekly (total of 9 doses)
Weeks 10 to 24 [First dose of the every-3-week dosing schedule is given at Week 10] | every three weeks (total of 5 doses)
Week 25 onwards until disease progression [First dose of the every-4-week dosing schedule is given at Week 25] | every four weeks

For dosing instructions of combination agents administered with DARZALEX see Clinical Studies (14.2)and manufacturer's prescribing information .

In Combination with Carfilzomib and Dexamethasone (DKd)

The recommended dosage for DARZALEX when administered in combination with carfilzomib and dexamethasone (4-week cycle) for patients with relapsed/refractory multiple myeloma is provided in Table 5.

Table 5: DARZALEX Dosing Schedule With Carfilzomib and Dexamethasone (4-Week Cycle)
Weeks | DARZALEX Dose [Based on actual body weight] | Schedule
Week 1 | 8 mg/kg | days 1 and 2 (total 2 doses)
Weeks 2 to 8 | 16 mg/kg | weekly (total of 7 doses)
Weeks 9 to 24 [First dose of the every-2-week dosing schedule is given at Week 9] | 16 mg/kg | every two weeks (total of 8 doses)
Week 25 onwards until disease progression [First dose of the every-4-week dosing schedule is given at Week 25] | 16 mg/kg | every four weeks

For dosing instructions of combination agents administered with DARZALEX see Clinical Studies (14.2)and manufacturer's prescribing information .

Infusion Rates

Administer DARZALEX intravenously at the infusion rate described below in Table 6. Consider incremental escalation of the infusion rate only in the absence of infusion-related reactions.

The recommended dose of 16 mg/kg to be administered on Day 1 when DARZALEX is administered as monotherapy or in combination may be split over two consecutive days, such that an 8 mg/kg dose is administered on Day 1 and Day 2, respectively.

Table 6: Infusion Rates for DARZALEX (16 mg/kg) Administration
 | Dilution volume | Initial rate (first hour) | Rate increment [Consider incremental escalation of the infusion rate only in the absence of infusion-related reactions.] | Maximum rate
Week 1 Infusion
Option 1 (Single dose infusion)
Week 1 Day 1 (16 mg/kg) | 1,000 mL | 50 mL/hour | 50 mL/hour every hour | 200 mL/hour
Option 2 (Split dose infusion)
Week 1 Day 1 (8 mg/kg) | 500 mL | 50 mL/hour | 50 mL/hour every hour | 200 mL/hour
Week 1 Day 2 (8 mg/kg) | 500 mL | 50 mL/hour | 50 mL/hour every hour | 200 mL/hour
Week 2 (16 mg/kg) [Use a dilution volume of 500 mL for the 16 mg/kg dose only if there were no infusion-related reactions the previous week. Otherwise, use a dilution volume of 1,000 mL.] | 500 mL | 50 mL/hour | 50 mL/hour every hour | 200 mL/hour
Week 3 onwards (16 mg/kg) [Use a modified initial rate (100 mL/hour) for subsequent infusions (i.e. Week 3 onwards) only if there were no infusion-related reactions during the previous infusion. Otherwise, continue to use instructions indicated in the table for the Week 2 infusion rate.] | 500 mL | 100 mL/hour | 50 mL/hour every hour | 200 mL/hour

Missed DARZALEX Doses

If a dose of DARZALEX is missed, administer the dose as soon as possible and adjust the dosing schedule to maintain the dosing interval.

2.3 Recommended Concomitant Medications

Pre-infusion Medication

Administer the following pre-infusion medications 1 hour to 3 hours before every DARZALEX infusion:

- Corticosteroid (long- or intermediate-acting)

Monotherapy:

Administer methylprednisolone 100 mg (or equivalent) intravenously. Following the second infusion, consider reducing the dose to 60 mg (or equivalent) administered either orally or intravenously.
In Combination:
Administer dexamethasone 20 mg (or equivalent) orally or intravenously.
When dexamethasone is the background regimen-specific corticosteroid, the dexamethasone dose that is part of the background regimen will serve as pre-medication on DARZALEX infusion days [see Clinical Studies (14)].
Do not administer background regimen-specific corticosteroids (e.g. prednisone) on DARZALEX infusion days when patients have received dexamethasone (or equivalent) as a pre-medication.

- Acetaminophen 650 mg to 1,000 mg orally
- Diphenhydramine 25 mg to 50 mg (or equivalent) orally or intravenously.

Post-infusion Medication

Administer the following post-infusion medications:

Monotherapy:
  Administer methylprednisolone 20 mg (or an equivalent dose of an intermediate- or long-acting corticosteroid) orally for 2 days starting the day after the administration of DARZALEX.
  In Combination:
  Consider administering oral methylprednisolone at a dose of less than or equal to 20 mg (or an equivalent dose of an intermediate- or long-acting corticosteroid) beginning the day after the administration of a DARZALEX infusion.
  If a background regimen-specific corticosteroid (e.g. dexamethasone, prednisone) is administered the day after the DARZALEX infusion, additional corticosteroids may not be needed [see Clinical Studies (14)].

For patients with a history of chronic obstructive pulmonary disease, consider prescribing short and long-acting bronchodilators and inhaled corticosteroids. Following the first 4 DARZALEX infusions, consider discontinuing these additional post-infusion medications, if the patient does not experience a major infusion-related reaction.

Prophylaxis for Herpes Zoster Reactivation

Initiate antiviral prophylaxis to prevent herpes zoster reactivation within 1 week after starting DARZALEX and continue for 3 months following the end of treatment [see Adverse Reactions (6.1)].

2.4 Dosage Modifications for Adverse Reactions

No dose reductions of DARZALEX are recommended. Consider withholding DARZALEX to allow recovery of blood cell counts in the event of myelosuppression [see Warnings and Precautions (5.3, 5.4)] .

For information concerning drugs given in combination with DARZALEX, see manufacturer's prescribing information.

Infusion-Related Reactions

For infusion-related reactions of any grade/severity, immediately interrupt the DARZALEX infusion and manage symptoms. Management of infusion-related reactions may further require reduction in the rate of infusion, or treatment discontinuation of DARZALEX as outlined below [see Warnings and Precautions (5.1)] .

- Grade 1–2 (mild to moderate): Once reaction symptoms resolve, resume the infusion at no more than half the rate at which the reaction occurred. If the patient does not experience any further reaction symptoms, infusion rate escalation may resume at increments and intervals as clinically appropriate up to the maximum rate of 200 mL/hour (Table 6).
- Grade 3 (severe): Once reaction symptoms resolve, consider restarting the infusion at no more than half the rate at which the reaction occurred. If the patient does not experience additional symptoms, resume infusion rate escalation at increments and intervals as outlined in Table 6. Repeat the procedure above in the event of recurrence of Grade 3 symptoms. Permanently discontinue DARZALEX upon the third occurrence of a Grade 3 or greater infusion-related reaction.
- Grade 4 (life-threatening): Permanently discontinue DARZALEX.

2.5 Preparation and Administration

Preparation

DARZALEX is for single dose only.

Prepare the solution for infusion using aseptic technique as follows:

- Calculate the dose (mg), total volume (mL) of DARZALEX solution required and the number of DARZALEX vials needed based on patient actual body weight.
- DARZALEX vials of the same strength with different NDCs are available and can be admixed in the same infusion bag [see Description (11), How Supplied/Storage and Handling (16)] .
- Check that the DARZALEX solution is colorless to pale yellow. Do not use if opaque particles, discoloration or other foreign particles are present.
- Remove a volume of 0.9% Sodium Chloride Injection from the infusion bag/container that is equal to the required volume of DARZALEX solution.
- Withdraw the necessary amount of DARZALEX solution and dilute to the appropriate volume by adding to the infusion bag/container containing 0.9% Sodium Chloride Injection as specified in Table 6 [see Dosage and Administration (2.2)] . Infusion bags/containers must be made of either polyvinylchloride (PVC), polypropylene (PP), polyethylene (PE) or polyolefin blend (PP+PE). Dilute under appropriate aseptic conditions. Discard any unused portion left in the vial.
- Gently invert the bag/container to mix the solution. Do not shake.
- Parenteral drug products should be inspected visually for particulate matter and discoloration prior to administration, whenever solution and container permit. The diluted solution may develop very small, translucent to white proteinaceous particles, as daratumumab is a protein. Do not use if visibly opaque particles, discoloration or foreign particles are observed.
- If not used immediately, store the diluted solution refrigerated for up to 24 hours at 2°C to 8°C (36°F to 46°F) and/or at room temperature up to 15 hours at 15°C to 25°C (59°F to 77°F). The room temperature storage includes infusion time. Protect from light during storage. Do not freeze.

Administration

- If stored in the refrigerator, allow the solution to come to room temperature. Administer the diluted solution by intravenous infusion using an infusion set fitted with a flow regulator and with an in-line, sterile, non-pyrogenic, low protein-binding polyethersulfone (PES) filter (pore size 0.22 micrometer or 0.2 micrometer). Administration sets must be made of either polyurethane (PU), polybutadiene (PBD), PVC, PP or PE.
- Do not store any unused portion of the infusion solution for reuse. Any unused product or waste material should be disposed of in accordance with local requirements.
- Do not infuse DARZALEX concomitantly in the same intravenous line with other agents.

3 DOSAGE FORMS AND STRENGTHS

DARZALEX is a colorless to pale yellow, preservative-free solution available as:

Injection:

- 100 mg/5 mL (20 mg/mL) in a single-dose vial.
- 400 mg/20 mL (20 mg/mL) in a single-dose vial.

4 CONTRAINDICATIONS

DARZALEX is contraindicated in patients with a history of severe hypersensitivity (e.g. anaphylactic reactions) to daratumumab or any of the components of the formulation [see Warnings and Precautions (5.1)] .

5 WARNINGS AND PRECAUTIONS

5.1 Infusion-Related Reactions

DARZALEX can cause severe and/or serious infusion-related reactions including anaphylactic reactions. These reactions can be life-threatening and fatal outcomes have been reported [see Adverse Reactions (6.2)] .

In clinical trials (monotherapy and combination: N=2,066), infusion-related reactions occurred in 37% of patients with the Week 1 (16 mg/kg) infusion, 2% with the Week 2 infusion, and cumulatively 6% with subsequent infusions. Less than 1% of patients had a Grade 3/4 infusion-related reaction at Week 2 or subsequent infusions. The median time to onset was 1.5 hours (range: 0 to 73 hours). The incidence of infusion modification due to reactions was 36%. Median durations of 16 mg/kg infusions for the Week 1, Week 2, and subsequent infusions were approximately 7, 4, and 3 hours respectively. Nearly all reactions occurred during infusion or within 4 hours of completing DARZALEX. Prior to the introduction of post-infusion medication in clinical trials, infusion-related reactions occurred up to 48 hours after infusion.

Severe reactions have occurred, including bronchospasm, hypoxia, dyspnea, hypertension, tachycardia, headache, laryngeal edema, pulmonary edema, and ocular adverse reactions, including choroidal effusion, acute myopia, and acute angle closure glaucoma. Signs and symptoms may include respiratory symptoms, such as nasal congestion, cough, throat irritation, as well as chills, vomiting and nausea. Less common signs and symptoms were wheezing, allergic rhinitis, pyrexia, chest discomfort, pruritus, hypotension, and blurred vision [see Adverse Reactions (6.1)] .

When DARZALEX dosing was interrupted in the setting of ASCT (CASSIOPEIA) for a median of 3.75 months (range: 2.4 to 6.9 months), upon re-initiation of DARZALEX, the incidence of infusion-related reactions was 11% for the first infusion following ASCT. Infusion rate/dilution volume used upon re-initiation was that used for the last DARZALEX infusion prior to interruption for ASCT. Infusion-related reactions occurring at re-initiation of DARZALEX following ASCT were consistent in terms of symptoms and severity (Grade 3 or 4: <1%) with those reported in previous studies at Week 2 or subsequent infusions.

In EQUULEUS, patients receiving combination treatment (n=97) were administered the first 16 mg/kg dose at Week 1 split over two days i.e. 8 mg/kg on Day 1 and Day 2, respectively. The incidence of any grade infusion-related reactions was 42%, with 36% of patients experiencing infusion-related reactions on Day 1 of Week 1, 4% on Day 2 of Week 1, and 8% with subsequent infusions. The median time to onset of a reaction was 1.8 hours (range: 0.1 to 5.4 hours). The incidence of infusion interruptions due to reactions was 30%. Median durations of infusions were 4.2 hours for Week 1-Day 1, 4.2 hours for Week 1-Day 2, and 3.4 hours for the subsequent infusions.

Pre-medicate patients with antihistamines, antipyretics and corticosteroids. Frequently monitor patients during the entire infusion [see Dosage and Administration (2.3)] . Interrupt DARZALEX infusion for reactions of any severity and institute medical management as needed. Permanently discontinue DARZALEX therapy if an anaphylactic reaction or life-threatening (Grade 4) reaction occurs and institute appropriate emergency care. For patients with Grade 1, 2, or 3 reactions, reduce the infusion rate when re-starting the infusion [see Dosage and Administration (2.4)] .

To reduce the risk of delayed infusion-related reactions, administer oral corticosteroids to all patients following DARZALEX infusions [see Dosage and Administration (2.3)] . Patients with a history of chronic obstructive pulmonary disease may require additional post-infusion medications to manage respiratory complications. Consider prescribing short- and long-acting bronchodilators and inhaled corticosteroids for patients with chronic obstructive pulmonary disease [see Dosage and Administration (2.3)] .

Ocular adverse reactions, including acute myopia and narrowing of the anterior chamber angle due to ciliochoroidal effusions with potential for increased intraocular pressure or glaucoma, have occurred with DARZALEX infusion. If ocular symptoms occur, interrupt DARZALEX infusion and seek immediate ophthalmologic evaluation prior to restarting DARZALEX.

5.2 Interference with Serological Testing

Daratumumab binds to CD38 on red blood cells (RBCs) and results in a positive Indirect Antiglobulin Test (Indirect Coombs test). Daratumumab-mediated positive indirect antiglobulin test may persist for up to 6 months after the last daratumumab infusion. Daratumumab bound to RBCs masks detection of antibodies to minor antigens in the patient's serum [see References (15)] . The determination of a patient's ABO and Rh blood type are not impacted [see Drug Interactions (7.1)] .

Notify blood transfusion centers of this interference with serological testing and inform blood banks that a patient has received DARZALEX. Type and screen patients prior to starting DARZALEX [see Dosage and Administration (2.1)] .

5.3 Neutropenia

DARZALEX may increase neutropenia induced by background therapy [see Adverse Reactions (6.1)].

Monitor complete blood cell counts periodically during treatment according to manufacturer's prescribing information for background therapies. Monitor patients with neutropenia for signs of infection. Consider withholding DARZALEX until recovery of neutrophils.

5.4 Thrombocytopenia

DARZALEX may increase thrombocytopenia induced by background therapy [see Adverse Reactions (6.1)].

Monitor complete blood cell counts periodically during treatment according to manufacturer's prescribing information for background therapies. Consider withholding DARZALEX until recovery of platelets.

5.5 Interference with Determination of Complete Response

Daratumumab is a human IgG kappa monoclonal antibody that can be detected on both, the serum protein electrophoresis (SPE) and immunofixation (IFE) assays used for the clinical monitoring of endogenous M-protein [see Drug Interactions (7.1)] . This interference can impact the determination of complete response and of disease progression in some patients with IgG kappa myeloma protein.

5.6 Embryo-Fetal Toxicity

Based on the mechanism of action, DARZALEX can cause fetal harm when administered to a pregnant woman. DARZALEX may cause depletion of fetal immune cells and decreased bone density. Advise pregnant women of the potential risk to a fetus. Advise females with reproductive potential to use effective contraception during treatment with DARZALEX and for 3 months after the last dose [see Use in Specific Populations (8.1, 8.3)] .

The combination of DARZALEX with lenalidomide, pomalidomide, or thalidomide is contraindicated in pregnant women, because lenalidomide, pomalidomide, and thalidomide may cause birth defects and death of the unborn child. Refer to the lenalidomide, pomalidomide, or thalidomide prescribing information on use during pregnancy.

6 ADVERSE REACTIONS

The following clinically significant adverse reactions are described elsewhere in the labeling:

- Infusion-related reactions [see Warnings and Precautions (5.1)] .
- Neutropenia [see Warnings and Precautions (5.3)] .
- Thrombocytopenia [see Warnings and Precautions (5.4)] .

6.1 Clinical Trials Experience

Because clinical trials are conducted under widely varying conditions, adverse reaction rates observed in the clinical trials of a drug cannot be directly compared to rates in the clinical trials of another drug and may not reflect the rates observed in practice.

The safety data described below reflects exposure to DARZALEX (16 mg/kg) in 2,459 patients with multiple myeloma including 2,303 patients who received DARZALEX in combination with background regimens and 156 patients who received DARZALEX as monotherapy. In this pooled safety population, the most common adverse reactions (≥20%) were upper respiratory infection, neutropenia, infusion-related reactions, thrombocytopenia, diarrhea, constipation, anemia, peripheral sensory neuropathy, fatigue, peripheral edema, nausea, cough, pyrexia, dyspnea, and asthenia.

Newly Diagnosed Multiple Myeloma Ineligible for Autologous Stem Cell Transplant

Combination Treatment with Lenalidomide and Dexamethasone (DRd)

The safety of DARZALEX in combination with lenalidomide and dexamethasone was evaluated in MAIA [see Clinical Studies (14.1)]. Adverse reactions described in Table 7 reflect exposure to DARZALEX for a median treatment duration of 25.3 months (range: 0.1 to 40.44 months) for daratumumab-lenalidomide-dexamethasone (DRd) and of 21.3 months (range: 0.03 to 40.64 months) for lenalidomide-dexamethasone (Rd).

Serious adverse reactions with a 2% greater incidence in the DRd arm compared to the Rd arm were pneumonia (DRd 15% vs Rd 8%), bronchitis (DRd 4% vs Rd 2%) and dehydration (DRd 2% vs Rd <1%).

Table 7: Adverse Reactions Reported in ≥10% of Patients and With at Least a 5% Greater Frequency in the DRd Arm in MAIA
Body System Adverse Reaction | DRd (N=364) |  |  | Rd (N=365)
Body System Adverse Reaction | All Grades (%) | Grade 3 (%) | Grade 4 (%) | All Grades (%) | Grade 3 (%) | Grade 4 (%)
Gastrointestinal disorders
Diarrhea | 57 | 7 | 0 | 46 | 4 | 0
Constipation | 41 | 1 | <1 | 36 | <1 | 0
Nausea | 32 | 1 | 0 | 23 | 1 | 0
Vomiting | 17 | 1 | 0 | 12 | <1 | 0
Infections
Upper respiratory tract infection [Acute sinusitis, Bacterial rhinitis, Laryngitis, Metapneumovirus infection, Nasopharyngitis, Oropharyngeal candidiasis, Pharyngitis, Respiratory syncytial virus infection, Respiratory tract infection, Respiratory tract infection viral, Rhinitis, Rhinovirus infection, Sinusitis, Tonsillitis, Tracheitis, Upper respiratory tract infection, Viral pharyngitis, Viral rhinitis, Viral upper respiratory tract infection] | 52 | 2 | <1 | 36 | 2 | <1
Bronchitis [Bronchiolitis, Bronchitis, Bronchitis viral, Respiratory syncytial virus bronchiolitis, Tracheobronchitis] | 29 | 3 | 0 | 21 | 1 | 0
Pneumonia [Atypical pneumonia, Bronchopulmonary aspergillosis, Lung infection, Pneumocystis jirovecii infection, Pneumocystis jirovecii pneumonia, Pneumonia, Pneumonia aspiration, Pneumonia pneumococcal, Pneumonia viral, Pulmonary mycosis] | 26 | 14 | 1 | 14 | 7 | 1
Urinary tract infection | 18 | 2 | 0 | 10 | 2 | 0
General disorders and administration site conditions
Infusion-related reactions [Infusion-related reaction includes terms determined by investigators to be related to infusion] | 41 | 2 | <1 | 0 | 0 | 0
Peripheral edema [Generalized edema, Gravitational edema, Edema, Peripheral edema, Peripheral swelling] | 41 | 2 | 0 | 33 | 1 | 0
Fatigue | 40 | 8 | 0 | 28 | 4 | 0
Asthenia | 32 | 4 | 0 | 25 | 3 | <1
Pyrexia | 23 | 2 | 0 | 18 | 2 | 0
Chills | 13 | 0 | 0 | 2 | 0 | 0
Musculoskeletal and connective tissue disorders
Back pain | 34 | 3 | <1 | 26 | 3 | <1
Muscle spasms | 29 | 1 | 0 | 22 | 1 | 0
Respiratory, thoracic and mediastinal disorders
Dyspnea [Dyspnea, Dyspnea exertional] | 32 | 3 | <1 | 20 | 1 | 0
Cough [Cough, Productive cough] | 30 | <1 | 0 | 18 | 0 | 0
Nervous system disorders
Peripheral sensory neuropathy | 24 | 1 | 0 | 15 | 0 | 0
Headache | 19 | 1 | 0 | 11 | 0 | 0
Paresthesia | 16 | 0 | 0 | 8 | 0 | 0
Metabolism and nutrition disorders
Decreased appetite | 22 | 1 | 0 | 15 | <1 | <1
Hyperglycemia | 14 | 6 | 1 | 8 | 3 | 1
Hypocalcemia | 14 | 1 | <1 | 9 | 1 | 1
Vascular disorders
Hypertension [Blood pressure increased, Hypertension] | 13 | 6 | <1 | 7 | 4 | 0
Key: D=daratumumab, Rd=lenalidomide-dexamethasone.

Laboratory abnormalities worsening during treatment from baseline listed in Table 8.

Table 8: Treatment-Emergent Hematology Laboratory Abnormalities in MAIA
 | DRd (N=364) |  |  | Rd (N=365)
 | All Grades (%) | Grade 3 (%) | Grade 4 (%) | All Grades (%) | Grade 3 (%) | Grade 4 (%)
Leukopenia | 90 | 30 | 5 | 82 | 20 | 4
Neutropenia | 91 | 39 | 17 | 77 | 28 | 11
Lymphopenia | 84 | 41 | 11 | 75 | 36 | 6
Thrombocytopenia | 67 | 6 | 3 | 58 | 7 | 4
Anemia | 47 | 13 | 0 | 57 | 24 | 0
Key: D=daratumumab, Rd=lenalidomide-dexamethasone.

Combination Treatment with Bortezomib, Melphalan and Prednisone

The safety of DARZALEX in combination with bortezomib, melphalan and prednisone was evaluated in ALCYONE [see Clinical Studies (14.1)]. Adverse reactions described in Table 9 reflect exposure to DARZALEX for a median treatment duration of 14.7 months (range: 0 to 25.8 months) for daratumumab, bortezomib, melphalan and prednisone (D-VMP) and of 12 months (range: 0.1 to 14.9 months) for VMP.

Serious adverse reactions with at least a 2% greater incidence in the D-VMP arm compared to the VMP arm were pneumonia (D-VMP 11% vs VMP 4%), upper respiratory tract infection (D-VMP 5% vs VMP 1%), and pulmonary edema (D-VMP 2% vs VMP 0%).

Table 9: Adverse Reactions Reported in ≥10% of Patients and With at Least a 5% Greater Frequency in the D-VMP Arm in ALCYONE
Body System Adverse Reaction | D-VMP (N=346) |  |  | VMP (N=354)
Body System Adverse Reaction | All Grades (%) | Grade 3 (%) | Grade 4 (%) | All Grades (%) | Grade 3 (%) | Grade 4 (%)
Infections
Upper respiratory tract infection [upper respiratory tract infection, bronchitis, bronchitis bacterial, epiglottitis, laryngitis, laryngitis bacterial, metapneumovirus infection, nasopharyngitis, oropharyngeal candidiasis, pharyngitis, pharyngitis streptococcal, respiratory syncytial virus infection, respiratory tract infection, respiratory tract infection viral, rhinitis, sinusitis, tonsillitis, tracheitis, tracheobronchitis, viral pharyngitis, viral rhinitis, viral upper respiratory tract infection] | 48 | 5 | 0 | 28 | 3 | 0
Pneumonia [pneumonia, lung infection, pneumonia aspiration, pneumonia bacterial, pneumonia pneumococcal, pneumonia streptococcal, pneumonia viral, and pulmonary sepsis] | 16 | 12 | < 1 | 6 | 5 | < 1
General disorders and administration site conditions
Infusion-related reactions [Infusion-related reaction includes terms determined by investigators to be related to infusion] | 28 | 4 | 1 | 0 | 0 | 0
Peripheral edema [edema peripheral, generalized edema, peripheral swelling] | 21 | 1 | < 1 | 14 | 1 | 0
Respiratory, thoracic and mediastinal disorders
Cough [cough, productive cough] | 16 | < 1 | 0 | 8 | < 1 | 0
Dyspnea [dyspnea, dyspnea exertional] | 13 | 2 | 1 | 5 | 1 | 0
Vascular disorders
Hypertension [hypertension, blood pressure increased] | 10 | 4 | < 1 | 3 | 2 | 0
Key: D=daratumumab, VMP=bortezomib-melphalan-prednisone.

Laboratory abnormalities worsening during treatment from baseline listed in Table 10.

Table 10: Treatment-Emergent Hematology Laboratory Abnormalities in ALCYONE
 | D-VMP (N=346) |  |  | VMP (N=354)
 | All Grades (%) | Grade 3 (%) | Grade 4 (%) | All Grades (%) | Grade 3 (%) | Grade 4 (%)
Thrombocytopenia | 88 | 27 | 11 | 88 | 26 | 16
Neutropenia | 86 | 34 | 10 | 87 | 32 | 11
Lymphopenia | 85 | 46 | 12 | 83 | 44 | 9
Anemia | 47 | 18 | 0 | 50 | 21 | 0
Key: D=daratumumab, VMP=bortezomib-melphalan-prednisone.

Newly Diagnosed Multiple Myeloma Eligible for Autologous Stem Cell Transplant

Combination Treatment with Bortezomib, Thalidomide and Dexamethasone (DVTd)

The safety of DARZALEX in combination with bortezomib, thalidomide and dexamethasone was evaluated in CASSIOPEIA [see Clinical Studies (14.1)]. Adverse reactions described in Table 11 reflect exposure to DARZALEX up to day 100 post-transplant. The median duration of induction/ASCT/consolidation treatment was 8.9 months (range: 7.0 to 12.0 months) for DVTd and 8.7 months (range: 6.4 to 11.5 months) for VTd.

Serious adverse reactions with a 2% greater incidence in the DVTd arm compared to the VTd arm were bronchitis (DVTd 2% vs VTd <1%) and pneumonia (DVTd 6% vs VTd 4%).

Table 11: Adverse Reactions Reported in ≥ 10% of Patients and With at Least a 5% Greater Frequency in the DVTd Arm in CASSIOPEIA
Body System Adverse Reaction | DVTd (N=536) |  |  | VTd (N=538)
Body System Adverse Reaction | All Grades (%) | Grade 3 (%) | Grade 4 (%) | All Grades (%) | Grade 3 (%) | Grade 4 (%)
General disorders and administration site conditions
Infusion-related reactions [Infusion-related reaction includes terms determined by investigators to be related to infusion] | 35 | 3 | <1 | 0 | 0 | 0
Pyrexia | 26 | 2 | <1 | 21 | 2 | 0
Gastrointestinal disorders
Nausea | 30 | 4 | 0 | 24 | 2 | <1
Vomiting | 16 | 2 | 0 | 10 | 2 | 0
Infections
Upper respiratory tract infection [Laryngitis, Laryngitis viral, Metapneumovirus infection, Nasopharyngitis, Oropharyngeal candidiasis, Pharyngitis, Respiratory syncytial virus infection, Respiratory tract infection, Respiratory tract infection viral, Rhinitis, Rhinovirus infection, Sinusitis, Tonsillitis, Tracheitis, Upper respiratory tract infection, Viral pharyngitis, Viral rhinitis, Viral upper respiratory tract infection] | 27 | 1 | 0 | 17 | 1 | 0
Bronchitis [Bronchiolitis, Bronchitis, Bronchitis chronic, Respiratory syncytial virus bronchitis, Tracheobronchitis] | 20 | 1 | 0 | 13 | 1 | 0
Respiratory, thoracic and mediastinal disorders
Cough [Cough, Productive cough] | 17 | 0 | 0 | 9 | 0 | 0
Vascular disorders
Hypertension | 10 | 4 | 0 | 5 | 2 | 0
Key: D=daratumumab, VTd=bortezomib-thalidomide -dexamethasone.
Note: Hematology laboratory related toxicities were excluded and reported separately in the table below.

Table 12: Treatment-Emergent Hematology Laboratory Abnormalities in CASSIOPEIA
 | DVTd (N=536) |  |  | VTd (N=538)
 | All Grades (%) | Grade 3 (%) | Grade 4 (%) | All Grades (%) | Grade 3 (%) | Grade 4 (%)
Lymphopenia | 95 | 44 | 15 | 91 | 37 | 10
Leukopenia | 82 | 14 | 10 | 57 | 6 | 9
Thrombocytopenia | 81 | 9 | 5 | 58 | 8 | 3
Neutropenia | 63 | 19 | 14 | 41 | 10 | 9
Anemia | 36 | 4 | 0 | 35 | 5 | 0
Key: D=daratumumab, VTd=bortezomib-thalidomide -dexamethasone.

Relapsed/Refractory Multiple Myeloma

Combination Treatment with Lenalidomide and Dexamethasone

The safety of DARZALEX in combination with lenalidomide and dexamethasone was evaluated in POLLUX [see Clinical Studies (14.2)]. Adverse reactions described in Table 13 reflect exposure to DARZALEX for a median treatment duration of 13.1 months (range: 0 to 20.7 months) for daratumumab-lenalidomide-dexamethasone (DRd) and of 12.3 months (range: 0.2 to 20.1 months) for lenalidomide-dexamethasone (Rd).

Serious adverse reactions occurred in 49% of patients in the DRd arm compared with 42% in the Rd arm. Serious adverse reactions with at least a 2% greater incidence in the DRd arm compared to the Rd arm were pneumonia (DRd 12% vs Rd 10%), upper respiratory tract infection (DRd 7% vs Rd 4%), influenza and pyrexia (DRd 3% vs Rd 1% for each).

Adverse reactions resulted in discontinuations for 7% (n=19) of patients in the DRd arm versus 8% (n=22) in the Rd arm.

Table 13: Adverse Reactions Reported in ≥ 10% of Patients and With at Least a 5% Greater Frequency in the DRd Arm in POLLUX
Adverse Reaction | DRd (N=283) |  |  | Rd (N=281)
Adverse Reaction | All Grades (%) | Grade 3 (%) | Grade 4 (%) | All Grades (%) | Grade 3 (%) | Grade 4 (%)
Infections
Upper respiratory tract infection [upper respiratory tract infection, bronchitis, sinusitis, respiratory tract infection viral, rhinitis, pharyngitis, respiratory tract infection, metapneumovirus infection, tracheobronchitis, viral upper respiratory tract infection, laryngitis, respiratory syncytial virus infection, staphylococcal pharyngitis, tonsillitis, viral pharyngitis, acute sinusitis, nasopharyngitis, bronchiolitis, bronchitis viral, pharyngitis streptococcal, tracheitis, upper respiratory tract infection bacterial, bronchitis bacterial, epiglottitis, laryngitis viral, oropharyngeal candidiasis, respiratory moniliasis, viral rhinitis, acute tonsillitis, rhinovirus infection] | 65 | 6 | < 1 | 51 | 4 | 0
General disorders and administration site conditions
Infusion-related reactions [Infusion-related reaction includes terms determined by investigators to be related to infusion] | 48 | 5 | 0 | 0 | 0 | 0
Fatigue | 35 | 6 | < 1 | 28 | 2 | 0
Pyrexia | 20 | 2 | 0 | 11 | 1 | 0
Gastrointestinal disorders
Diarrhea | 43 | 5 | 0 | 25 | 3 | 0
Nausea | 24 | 1 | 0 | 14 | 0 | 0
Vomiting | 17 | 1 | 0 | 5 | 1 | 0
Respiratory, thoracic and mediastinal disorders
Cough [cough, productive cough, allergic cough] | 30 | 0 | 0 | 15 | 0 | 0
Dyspnea [dyspnea, dyspnea exertional] | 21 | 3 | < 1 | 12 | 1 | 0
Musculoskeletal and connective tissue disorders
Muscle spasms | 26 | 1 | 0 | 19 | 2 | 0
Nervous system disorders
Headache | 13 | 0 | 0 | 7 | 0 | 0
Key: D=daratumumab, Rd=lenalidomide-dexamethasone.

Laboratory abnormalities worsening during treatment from baseline listed in Table 14.

Table 14: Treatment-Emergent Hematology Laboratory Abnormalities in POLLUX
 | DRd (N=283) |  |  | Rd (N=281)
 | All Grades (%) | Grade 3 (%) | Grade 4 (%) | All Grades (%) | Grade 3 (%) | Grade 4 (%)
Lymphopenia | 95 | 42 | 10 | 87 | 32 | 6
Neutropenia | 92 | 36 | 17 | 87 | 32 | 8
Thrombocytopenia | 73 | 7 | 6 | 67 | 10 | 5
Anemia | 52 | 13 | 0 | 57 | 19 | 0
Key: D=daratumumab, Rd=lenalidomide-dexamethasone.

Combination Treatment with Bortezomib and Dexamethasone

The safety of DARZALEX in combination with bortezomib and dexamethasone was evaluated in CASTOR [see Clinical Studies (14.2)]. Adverse reactions described in Table 15 reflect exposure to DARZALEX for a median treatment duration of 6.5 months (range: 0 to 14.8 months) for daratumumab-bortezomib-dexamethasone (DVd) and of 5.2 months (range: 0.2 to 8.0 months) for bortezomib-dexamethasone (Vd) arm.

Serious adverse reactions occurred in 42% of patients in the DVd arm compared with 34% in the Vd arm. Serious adverse reactions with at least a 2% greater incidence in the DVd arm compared to the Vd arm were upper respiratory tract infection (DVd 5% vs Vd 2%), diarrhea and atrial fibrillation (DVd 2% vs Vd 0% for each).

Adverse reactions resulted in discontinuations for 7% (n=18) of patients in the DVd arm versus 9% (n=22) in the Vd arm.

Table 15: Adverse Reactions Reported in ≥10% of Patients and With at Least a 5% Greater Frequency in the DVd Arm CASTOR
Adverse Reaction | DVd (N=243) |  |  | Vd (N=237)
Adverse Reaction | All Grades (%) | Grade 3 (%) | Grade 4 (%) | All Grades (%) | Grade 3 (%) | Grade 4 (%)
Nervous system disorders
Peripheral sensory neuropathy | 47 | 5 | 0 | 38 | 6 | < 1
General disorders and administration site conditions
Infusion-related reactions [Infusion-related reaction includes terms determined by investigators to be related to infusion] | 45 | 9 | 0 | 0 | 0 | 0
Peripheral edema [edema peripheral, edema, generalized edema, peripheral swelling] | 22 | 1 | 0 | 13 | 0 | 0
Pyrexia | 16 | 1 | 0 | 11 | 1 | 0
Infections
Upper respiratory tract infection [upper respiratory tract infection, bronchitis, sinusitis, respiratory tract infection viral, rhinitis, pharyngitis, respiratory tract infection, metapneumovirus infection, tracheobronchitis, viral upper respiratory tract infection, laryngitis, respiratory syncytial virus infection, staphylococcal pharyngitis, tonsillitis, viral pharyngitis, acute sinusitis, nasopharyngitis, bronchiolitis, bronchitis viral, pharyngitis streptococcal, tracheitis, upper respiratory tract infection bacterial, bronchitis bacterial, epiglottitis, laryngitis viral, oropharyngeal candidiasis, respiratory moniliasis, viral rhinitis, acute tonsillitis, rhinovirus infection] | 44 | 6 | 0 | 30 | 3 | < 1
Gastrointestinal disorders
Diarrhea | 32 | 3 | < 1 | 22 | 1 | 0
Vomiting | 11 | 0 | 0 | 4 | 0 | 0
Respiratory, thoracic and mediastinal disorders
Cough [cough, productive cough, allergic cough] | 27 | 0 | 0 | 14 | 0 | 0
Dyspnea [dyspnea, dyspnea exertional] | 21 | 4 | 0 | 11 | 1 | 0
Key: D=daratumumab, Vd=bortezomib-dexamethasone.

Laboratory abnormalities worsening during treatment are listed in Table 16.

Table 16: Treatment-Emergent Hematology Laboratory Abnormalities in CASTOR
 | DVd (N=243) |  |  | Vd (N=237)
 | All Grades (%) | Grade 3 (%) | Grade 4 (%) | All Grades (%) | Grade 3 (%) | Grade 4 (%)
Thrombocytopenia | 90 | 28 | 19 | 85 | 22 | 13
Lymphopenia | 89 | 41 | 7 | 81 | 24 | 3
Neutropenia | 58 | 12 | 3 | 40 | 5 | < 1
Anemia | 48 | 13 | 0 | 56 | 14 | 0
Key: D=daratumumab, Vd=bortezomib-dexamethasone.

Combination Treatment with Twice-Weekly (20/56 mg/m^2) Carfilzomib and Dexamethasone

The safety of DARZALEX in combination with twice weekly carfilzomib and dexamethasone was evaluated in CANDOR [see Clinical Studies (14.2)] . Adverse reactions described in Table 17 reflect exposure to DARZALEX for a median treatment duration of 16.1 months (range: 0.1 to 23.7 months) for the daratumumab-carfilzomib-dexamethasone (DKd) group and median treatment duration of 9.3 months (range: 0.1 to 22.4 months) for the carfilzomib-dexamethasone group (Kd).

Serious adverse reactions occurred in 56% of patients who received DARZALEX in combination with Kd and 46% of patients who received Kd. The most frequent serious adverse reactions reported in the DKd arm as compared with the Kd arm were pneumonia (DKd 14% vs Kd 9%), pyrexia (DKd 4.2% vs Kd 2.0%), influenza (DKd 3.9% vs Kd 1.3%), sepsis (DKd 3.9% vs Kd 1.3%), anemia (DKd 2.3% vs Kd 0.7%), bronchitis (DKd 1.9% vs Kd 0%), and diarrhea (DKd 1.6% vs Kd 0%). Fatal adverse reactions within 30 days of the last dose of any study treatment occurred in 10% of 308 patients who received DARZALEX in combination with Kd versus 5% of 153 patients who received Kd. The most frequent fatal adverse reaction was infection (4.5% vs 2.6%).

Permanent discontinuation of DARZALEX due to an adverse reaction occurred in 9% of patients. Adverse reactions (>1%) which resulted in permanent discontinuation of DARZALEX included pneumonia.

Infusion-related reactions that occurred on the day of administration of any DARZALEX dose or on the next day occurred in 18% of patients and that occurred on the day of administration of the first DARZALEX dose or the next day occurred in 12%.

Table 17: Adverse Reactions (≥15%) in Patients Who Received DARZALEX in Combination with Carfilzomib and Dexamethasone (DKd) in CANDOR
Adverse Reaction | DKd (N=308) |  | Kd (N=153)
Adverse Reaction | All Grades | Grades 3 or 4 | All Grades | Grades 3 or 4
Adverse Reaction | (%) | (%) | (%) | (%)
General Disorders and Administration Site Conditions
Infusion-related reactions [The incidence of infusion-related reactions is based on a group of symptoms (including hypertension, pyrexia, rash, myalgia, hypotension, blood pressure increased, urticaria, acute kidney injury, bronchospasm, face edema, hypersensitivity, rash, syncope, wheezing, eye pruritus, eyelid edema, renal failure, swelling face) related to infusion reactions which occurred within 1 day after DKd or Kd administration.] | 41 | 12 | 28 | 5
Fatigue [Fatigue includes fatigue and asthenia.] | 32 | 11 | 28 | 8
Pyrexia | 20 | 1.9 | 15 | 0.7
Infections
Respiratory tract infection [Respiratory tract infection includes respiratory tract infection, lower respiratory tract infection, upper respiratory tract infection and viral upper respiratory tract infection.] | 40 [Includes fatal adverse reactions.] | 7 | 29 | 3.3
Pneumonia | 18 | 13 | 12 | 9
Bronchitis | 17 | 2.6 | 12 | 1.3
Blood and lymphatic system disorders
Thrombocytopenia [Thrombocytopenia includes platelet count decreased and thrombocytopenia.] | 37 | 25 | 30 | 16
Anemia [Anemia includes anemia, hematocrit decreased and hemoglobin decreased.] | 33 | 17 | 31 | 14
Gastrointestinal disorders
Diarrhea | 32 | 3.9 | 14 | 0.7
Nausea | 18 | 0 | 13 | 0.7
Vascular Disorders
Hypertension | 31 | 18 | 28 | 13
Respiratory, Thoracic and Mediastinal Disorders
Cough [Cough includes productive cough and cough.] | 21 | 0 | 21 | 0
Dyspnea | 20 | 3.9 | 22 | 2.6
Psychiatric disorders
Insomnia | 18 | 3.9 | 11 | 2
Musculoskeletal and connective tissue disorders
Back pain | 16 | 1.9 | 10 | 1.3
Key: D=daratumumab; Kd=carfilzomib-dexamethasone.

Adverse Reactions Occurring at a Frequency of < 15%

- Blood and lymphatic system disorders: neutropenia, lymphopenia, leukopenia, febrile neutropenia
- Cardiac disorders: atrial fibrillation
- Gastrointestinal disorders: vomiting, constipation
- General disorders and administration site conditions: peripheral edema, asthenia, chills
- Infections: influenza, urinary tract infection, sepsis, septic shock
- Metabolism and nutrition disorders: decreased appetite, hyperglycemia, hypocalcemia, dehydration
- Musculoskeletal and connective tissue disorders: muscle spasms, arthralgia, musculoskeletal chest pain
- Nervous system disorders: headache, dizziness, peripheral sensory neuropathy, paresthesia, posterior reversible encephalopathy syndrome
- Respiratory, thoracic and mediastinal disorders: pulmonary edema
- Skin and subcutaneous tissue disorders: rash, pruritus

Combination Treatment with Once-Weekly (20/70 mg/m^2) Carfilzomib and Dexamethasone

The safety of DARZALEX in combination with once-weekly carfilzomib and dexamethasone was evaluated in EQUULEUS [see Clinical Studies (14.2)] . Adverse reactions described in Table 18 reflect exposure to DARZALEX for a median treatment duration of 19.8 months (range: 0.3 to 34.5 months).

Serious adverse reactions were reported in 48% of patients. The most frequent serious adverse reactions reported were pneumonia (4.7%), upper respiratory tract infection (4.7%), basal cell carcinoma (4.7%), influenza (3.5%), general physical health deterioration (3.5%), and hypercalcemia (3.5%). Fatal adverse reactions within 30 days of the last dose of any study treatment occurred in 3.5% of patients who died of general physical health deterioration, multi-organ failure secondary to pulmonary aspergillosis, and disease progression.

Permanent discontinuation of DARZALEX due to an adverse reaction occurred in 8% of patients. No adverse reactions which resulted in permanent discontinuation of DARZALEX occurred in more than one patient.

Infusion-related reactions that occurred on the day of administration of any DARZALEX dose or on the next day occurred in 44% of patients. For patients who received the split first dose of DARZALEX, infusion-related reactions that occurred in 36% and 4% on the first and second day of administration of DARZALEX, respectively.

Table 18: Adverse Reactions (≥15%) of Patients Who Received DARZALEX in Combination with Carfilzomib and Dexamethasone in EQUULEUS
Adverse Reaction | DKd (N=85)
Adverse Reaction | All Grades (%) | Grades 3 or 4 (%)
Blood and lymphatic system disorders
Thrombocytopenia [Thrombocytopenia includes platelet count decreased and thrombocytopenia.] | 68 | 32
Anemia [Anemia includes anemia, hematocrit decreased and hemoglobin decreased.] | 52 | 21
Neutropenia [Neutropenia includes neutrophil count decreased and neutropenia.] | 31 | 21
Lymphopenia [Lymphopenia includes lymphocyte count decreased and lymphopenia] | 29 | 25
General disorder and administration site conditions
Fatigue [Fatigue includes fatigue and asthenia.] | 54 | 18
Infusion-related reactions [The incidence of infusion-related reactions is based on a group of symptoms (including hypertension, pyrexia, rash, myalgia, hypotension, blood pressure increased, urticaria, acute kidney injury, bronchospasm, face edema, hypersensitivity, rash, syncope, wheezing, eye pruritus, eyelid edema, renal failure, swelling face) related to infusion reactions which occurred within 1 day after DKd administration.] | 53 | 12
Pyrexia | 37 | 1.2
Infections
Respiratory tract infection [Respiratory tract infection includes respiratory tract infection, lower respiratory tract infection, upper respiratory tract infection and viral upper respiratory tract infection.] | 53 | 3.5
Bronchitis | 19 | 0
Nasopharyngitis | 18 | 0
Influenza | 17 | 3.5
Gastrointestinal disorders
Nausea | 42 | 1.2
Vomiting | 40 | 1.2
Diarrhea | 38 | 2.4
Constipation | 17 | 0
Respiratory, thoracic and mediastinal disorders
Dyspnea | 35 | 3.5
Cough [Cough includes productive cough and cough.] | 33 | 0
Vascular disorders
Hypertension | 33 | 20
Psychiatric disorders
Insomnia | 33 | 4.7
Nervous system disorders
Headache | 27 | 1.2
Musculoskeletal and connective tissue disorders
Back pain | 25 | 0
Pain in extremity | 15 | 0
Key: D=daratumumab; Kd=carfilzomib-dexamethasone.

Adverse Reactions Occurring at a Frequency of < 15%

- Blood and lymphatic system disorders: leukopenia, febrile neutropenia
- Cardiac disorders: atrial fibrillation
- Gastrointestinal disorders: pancreatitis
- General disorders and administration site conditions: peripheral edema, chills
- Infections: pneumonia, urinary tract infection, sepsis, septic shock
- Metabolism and nutrition disorders: decreased appetite, hyperglycemia, dehydration, hypocalcemia
- Musculoskeletal and connective tissue disorders: muscle spasms, musculoskeletal chest pain, arthralgia
- Nervous system disorders: dizziness, paresthesia, peripheral sensory neuropathy
- Skin and subcutaneous tissue disorders: pruritus, rash

Combination Treatment with Pomalidomide and Dexamethasone

The safety of DARZALEX in combination with pomalidomide and dexamethasone was evaluated in EQUULEUS [see Clinical Studies (14.2)] . Adverse reactions described in Table 19 reflect exposure to DARZALEX, pomalidomide and dexamethasone (DPd) for a median treatment duration of 6 months (range: 0.03 to 16.9 months).

The overall incidence of serious adverse reactions was 49%. Serious adverse reactions reported in ≥5% patients included pneumonia (7%). Adverse reactions resulted in discontinuations for 13% of patients.

Table 19: Adverse Reactions With Incidence ≥10% Reported in EQUULEUS
Adverse Reaction | DPd (N=103)
Adverse Reaction | All Grades (%) | Grade 3 (%) | Grade 4 (%)
General disorders and administration site conditions
Fatigue | 50 | 10 | 0
Infusion-related reactions [Infusion-related reaction includes terms determined by investigators to be related to infusion] | 50 | 4 | 0
Pyrexia | 25 | 1 | 0
Chills | 20 | 0 | 0
Edema peripheral [edema, edema peripheral, peripheral swelling] | 17 | 4 | 0
Asthenia | 15 | 0 | 0
Non-cardiac chest pain | 15 | 0 | 0
Pain | 11 | 0 | 0
Infections
Upper respiratory tract infection [acute tonsillitis, bronchitis, laryngitis, nasopharyngitis, pharyngitis, respiratory syncytial virus infection, rhinitis, sinusitis, tonsillitis, upper respiratory tract infection] | 50 | 4 | 1
Pneumonia [lung infection, pneumonia, pneumonia aspiration] | 15 | 8 | 2
Respiratory, thoracic and mediastinal disorders
Cough [cough, productive cough, allergic cough] | 43 | 1 | 0
Dyspnea [dyspnea, dyspnea exertional] | 33 | 6 | 1
Nasal congestion | 16 | 0 | 0
Gastrointestinal disorders
Diarrhea | 38 | 3 | 0
Constipation | 33 | 0 | 0
Nausea | 30 | 0 | 0
Vomiting | 21 | 2 | 0
Musculoskeletal and connective tissue disorders
Muscle spasms | 26 | 1 | 0
Back pain | 25 | 6 | 0
Arthralgia | 22 | 2 | 0
Pain in extremity | 15 | 0 | 0
Bone pain | 13 | 4 | 0
Musculoskeletal chest pain | 13 | 2 | 0
Psychiatric disorders
Insomnia | 23 | 2 | 0
Anxiety | 13 | 0 | 0
Nervous system disorders
Dizziness | 21 | 2 | 0
Tremor | 19 | 3 | 0
Headache | 17 | 0 | 0
Metabolism and nutrition disorders
Hypokalemia | 16 | 3 | 0
Hyperglycemia | 13 | 5 | 1
Decreased appetite | 11 | 0 | 0
Key: D=daratumumab, Pd=pomalidomide-dexamethasone.

Laboratory abnormalities worsening during treatment are listed in Table 20.

Table 20: Treatment-Emergent Hematology Laboratory Abnormalities in EQUULEUS
 | DPd (N=103)
 | All Grades (%) | Grade 3 (%) | Grade 4 (%)
Neutropenia | 95 | 36 | 46
Lymphopenia | 94 | 45 | 26
Thrombocytopenia | 75 | 10 | 10
Anemia | 57 | 30 | 0
Key: D=daratumumab, Pd=pomalidomide-dexamethasone.

Monotherapy

The safety of DARZALEX was evaluated in 156 adult patients with relapsed and refractory multiple myeloma in three open-label, clinical trials. Patients received DARZALEX 16 mg/kg. The median duration of exposure was 3.3 months (range: 0.03 to 20.04 months).

Serious adverse reactions were reported in 51 (33%) patients. The most frequent serious adverse reactions were pneumonia (6%), general physical health deterioration (3%), and pyrexia (3%).

Adverse reactions resulted in treatment delay for 24 (15%) patients, most frequently for infections. Adverse reactions resulted in discontinuations for 6 (4%) patients.

Adverse reactions occurring in at least 10% of patients are presented in Table 21. Table 22 describes Grade 3–4 laboratory abnormalities reported at a rate of ≥10%.

Table 21: Adverse Reactions With Incidence ≥10% in Patients With Multiple Myeloma Treated With DARZALEX 16 mg/kg
Adverse Reaction | DARZALEX (N=156)
Adverse Reaction | All Grades (%) | Grade 3 (%) | Grade 4 (%)
General disorders and administration site conditions
Infusion-related reaction [Infusion-related reaction includes terms determined by investigators to be related to infusion] | 48 | 3 | 0
Fatigue | 39 | 2 | 0
Pyrexia | 21 | 1 | 0
Chills | 10 | 0 | 0
Gastrointestinal disorders
Nausea | 27 | 0 | 0
Diarrhea | 16 | 1 | 0
Constipation | 15 | 0 | 0
Vomiting | 14 | 0 | 0
Musculoskeletal and connective tissue disorders
Back pain | 23 | 2 | 0
Arthralgia | 17 | 0 | 0
Pain in extremity | 15 | 1 | 0
Musculoskeletal chest pain | 12 | 1 | 0
Respiratory, thoracic and mediastinal disorders
Cough | 21 | 0 | 0
Nasal congestion | 17 | 0 | 0
Dyspnea | 15 | 1 | 0
Infections
Upper respiratory tract infection | 20 | 1 | 0
Nasopharyngitis | 15 | 0 | 0
Pneumonia [Pneumonia also includes the terms streptococcal pneumonia and lobar pneumonia.] | 11 | 6 | 0
Metabolism and nutrition disorders
Decreased appetite | 15 | 1 | 0
Nervous system disorders
Headache | 12 | 1 | 0
Vascular disorders
Hypertension | 10 | 5 | 0

Table 22: Treatment-Emergent Grade 3–4 Laboratory Abnormalities (≥10%)
 | Daratumumab 16 mg/kg (N=156)
 | All Grades (%) | Grade 3 (%) | Grade 4 (%)
Lymphopenia | 72 | 30 | 10
Neutropenia | 60 | 17 | 3
Thrombocytopenia | 48 | 10 | 8
Anemia | 45 | 19 | 0

Herpes Zoster Virus Reactivation

Prophylaxis for Herpes Zoster Virus reactivation was recommended for patients in some clinical trials of DARZALEX. In monotherapy studies, herpes zoster was reported in 3% of patients. In the combination therapy studies, herpes zoster was reported in 2–5% of patients receiving DARZALEX.

Infections

Grade 3 or 4 infections were reported as follows:

- Relapsed/refractory patient studies: DVd: 21% vs. Vd: 19%; DRd: 28% vs. Rd: 23%; DPd: 28%; DKd [where carfilzomib 20/56 mg/m^2 was administered twice-weekly] : 37%, Kd : 29%; DKd [where carfilzomib 20/70 mg/m^2 was administered once-weekly] : 21%
- Newly diagnosed patient studies: D-VMP: 23%, VMP: 15%; DRd: 32%, Rd: 23%; DVTd: 22%; VTd: 20%.

Pneumonia was the most commonly reported severe (Grade 3 or 4) infection across studies. In active controlled studies, discontinuations from treatment due to infections occurred in 1–4% of patients.

Fatal infections (Grade 5) were reported as follows:

- Relapsed/refractory patient studies: DVd: 1%, Vd: 2%; DRd: 2%, Rd: 1%; DPd: 2%; DKd : 5%, Kd : 3%; DKd : 0%
- Newly diagnosed patient studies: D-VMP: 1%, VMP: 1%; DRd: 2%, Rd: 2%; DVTd: 0%, VTd: 0%.

Fatal infections were generally infrequent and balanced between the DARZALEX containing regimens and active control arms. Fatal infections were primarily due to pneumonia and sepsis.

Hepatitis B Virus (HBV) Reactivation

Hepatitis B virus reactivation has been reported in less than 1% of patients (including fatal cases) treated with DARZALEX in clinical trials.

Other Clinical Trials Experience

The following adverse reactions have been reported following administration of daratumumab and hyaluronidase for subcutaneous injection:

Nervous System disorders: Syncope

6.2 Postmarketing Experience

The following adverse reactions have been identified during post-approval use of daratumumab. Because these reactions are reported voluntarily from a population of uncertain size, it is not always possible to reliably estimate their frequency or establish a causal relationship to drug exposure.

Immune System disorders: Anaphylactic reaction, IRR (including deaths)

Gastrointestinal disorders: Pancreatitis

Infections: Cytomegalovirus, Listeriosis

7 DRUG INTERACTIONS

7.1 Effects of Daratumumab on Laboratory Tests

Interference with Indirect Antiglobulin Tests (Indirect Coombs Test)

Daratumumab binds to CD38 on RBCs and interferes with compatibility testing, including antibody screening and cross matching. Daratumumab interference mitigation methods include treating reagent RBCs with dithiothreitol (DTT) to disrupt daratumumab binding [see References (15)] or genotyping. Since the Kell blood group system is also sensitive to DTT treatment, supply K-negative units after ruling out or identifying alloantibodies using DTT-treated RBCs.

If an emergency transfusion is required, administer non-cross-matched ABO/RhD-compatible RBCs per local blood bank practices.

Interference with Serum Protein Electrophoresis and Immunofixation Tests

Daratumumab may be detected on serum protein electrophoresis (SPE) and immunofixation (IFE) assays used for monitoring disease monoclonal immunoglobulins (M protein). False positive SPE and IFE assay results may occur for patients with IgG kappa myeloma protein impacting initial assessment of complete responses by International Myeloma Working Group (IMWG) criteria. In patients with persistent very good partial response, where daratumumab interference is suspected, consider using a FDA-approved daratumumab-specific IFE assay to distinguish daratumumab from any remaining endogenous M protein in the patient's serum, to facilitate determination of a complete response.

8 USE IN SPECIFIC POPULATIONS

8.1 Pregnancy

Risk Summary

DARZALEX can cause fetal harm when administered to a pregnant woman. The assessment of associated risks with daratumumab products is based on the mechanism of action and data from target antigen CD38 knockout animal models (see Data) . There are no available data on the use of DARZALEX in pregnant women to evaluate drug-associated risk of major birth defects, miscarriage or adverse maternal or fetal outcomes. Animal reproduction studies have not been conducted.

The estimated background risk of major birth defects and miscarriage for the indicated population is unknown. All pregnancies have a background risk of birth defect, loss, or other adverse outcomes. In the U.S. general population, the estimated background risk of major birth defects and miscarriage in clinically recognized pregnancies is 2% to 4% and 15% to 20%, respectively.

The combination of DARZALEX and lenalidomide, pomalidomide, or thalidomide is contraindicated in pregnant women, because lenalidomide, pomalidomide, and thalidomide may cause birth defects and death of the unborn child. Lenalidomide, pomalidomide, and thalidomide are only available through a REMS program. Refer to the lenalidomide, pomalidomide, or thalidomide prescribing information on use during pregnancy.

Clinical Considerations

Fetal/Neonatal Adverse Reactions

Immunoglobulin G1 (IgG1) monoclonal antibodies are transferred across the placenta. Based on its mechanism of action, DARZALEX may cause depletion of fetal CD38 positive immune cells and decreased bone density. Defer administering live vaccines to neonates and infants exposed to DARZALEX in utero until a hematology evaluation is completed.

Data

Animal Data

Mice that were genetically modified to eliminate all CD38 expression (CD38 knockout mice) had reduced bone density at birth that recovered by 5 months of age. Data from studies using CD38 knockout animal models also suggest the involvement of CD38 in regulating humoral immune responses (mice), feto-maternal immune tolerance (mice), and early embryonic development (frogs).

8.2 Lactation

Risk Summary

There is no data on the presence of daratumumab in human milk, the effects on the breastfed child, or the effects on milk production. Maternal immunoglobulin G is known to be present in human milk. Published data suggest that antibodies in breast milk do not enter the neonatal and infant circulations in substantial amounts. Because of the potential for serious adverse reactions in the breastfed child when DARZALEX is administered with lenalidomide, pomalidomide, or thalidomide, advise women not to breastfeed during treatment with DARZALEX. Refer to lenalidomide, pomalidomide, or thalidomide prescribing information for additional information.

8.3 Females and Males of Reproductive Potential

DARZALEX can cause fetal harm when administered to a pregnant woman [see Use in Specific Populations (8.1)] .

Pregnancy Testing

With the combination of DARZALEX with lenalidomide, pomalidomide, or thalidomide, refer to the lenalidomide, pomalidomide, or thalidomide labeling for pregnancy testing requirements prior to initiating treatment in females of reproductive potential.

Contraception

Advise females of reproductive potential to use effective contraception during treatment with DARZALEX and for 3 months after the last dose. Additionally, refer to the lenalidomide, pomalidomide, or thalidomide labeling for additional recommendations for contraception.

8.4 Pediatric Use

Safety and effectiveness of DARZALEX in pediatric patients have not been established.

The safety and effectiveness of DARZALEX in combination with chemotherapy were assessed but not established in a single open-label trial (DELPHINUS; NCT03384654) in 34 pediatric patients (2 to <17 years of age) with relapsed/refractory acute lymphoblastic leukemia or lymphoblastic lymphoma. No new safety signals were observed in these pediatric patients. The pharmacokinetic parameters in these pediatric patients were within range of values previously observed in adults with multiple myeloma given the same dose based on body weight.

8.5 Geriatric Use

Of the 2,459 patients who received DARZALEX at the recommended dose, 38% were 65 to 74 years of age, and 15% were 75 years of age and older. No overall differences in effectiveness were observed between these patients and younger patients. The incidence of serious adverse reactions was higher in older than in younger patients [see Adverse Reactions (6.1)] . Among patients with relapsed and refractory multiple myeloma (n=1,213), the serious adverse reactions that occurred more frequently in patients 65 years and older were pneumonia and sepsis. Within the DKd group in CANDOR, fatal adverse reactions occurred in 14% of patients 65 years and older compared to 6% of patients less than 65 years. Among patients with newly diagnosed multiple myeloma who are ineligible for autologous stem cell transplant (n=710), the serious adverse reaction that occurred more frequently in patients 75 years and older was pneumonia.

11 DESCRIPTION

Daratumumab is an immunoglobulin G1 kappa (IgG1κ) human monoclonal antibody that binds to CD38 antigen. It is produced in Chinese Hamster Ovary (CHO) cells using recombinant DNA technology. The molecular weight of daratumumab is approximately 148 kDa.

DARZALEX®(daratumumab) injection is supplied as a colorless to pale yellow preservative-free solution for intravenous use in a single-dose vial. The pH is 5.5.

Each DARZALEX 20 mL single-dose vial contains (NDC 57894-502-20) 400 mg daratumumab, glacial acetic acid (3.7 mg), mannitol (510 mg), polysorbate 20 (8 mg), sodium acetate trihydrate (59.3 mg), sodium chloride (70.1 mg), and Water for Injection, USP.

Each DARZALEX 5 mL single-dose vial contains (NDC 57894-502-05) 100 mg daratumumab, glacial acetic acid (0.9 mg), mannitol (127.5 mg), polysorbate 20 (2 mg), sodium acetate trihydrate (14.8 mg), sodium chloride (17.5 mg), and Water for Injection, USP.

Each DARZALEX 20 mL single-dose vial contains (NDC 57894-505-20) 400 mg daratumumab, L-histidine (7 mg), L-histidine hydrochloride monohydrate (32.6 mg), L-methionine (20 mg), polysorbate 20 (8 mg), sorbitol (1093 mg), and Water for Injection, USP.

Each DARZALEX 5 mL single-dose vial contains (NDC 57894-505-05) 100 mg daratumumab, L-histidine (1.8 mg), L-histidine hydrochloride monohydrate (8.2 mg), L-methionine (5 mg), polysorbate 20 (2 mg), sorbitol (273.3 mg), and Water for Injection, USP.

12 CLINICAL PHARMACOLOGY

12.1 Mechanism of Action

CD38 is a transmembrane glycoprotein (48 kDa) expressed on the surface of hematopoietic cells, including multiple myeloma and other cell types and tissues and has multiple functions, such as receptor mediated adhesion, signaling, and modulation of cyclase and hydrolase activity. Daratumumab is an IgG1κ human monoclonal antibody (mAb) that binds to CD38 and inhibits the growth of CD38 expressing tumor cells by inducing apoptosis directly through Fc mediated cross linking as well as by immune-mediated tumor cell lysis through complement dependent cytotoxicity (CDC), antibody dependent cell mediated cytotoxicity (ADCC) and antibody dependent cellular phagocytosis (ADCP). A subset of myeloid derived suppressor cells (CD38+MDSCs), regulatory T cells (CD38+Tregs) and B cells (CD38+Bregs) are decreased by daratumumab.

12.2 Pharmacodynamics

NK cells express CD38 and are susceptible to daratumumab mediated cell lysis. Decreases in absolute counts and percentages of total NK cells (CD16+CD56+) and activated (CD16+CD56dim) NK cells in peripheral whole blood and bone marrow were observed with DARZALEX treatment.

Exposure-Response Relationship

The exposure-response relationship and time course of pharmacodynamics of DARZALEX have not been fully characterized.

Cardiac Electrophysiology

DARZALEX as a large protein has a low likelihood of direct ion channel interactions. There is no evidence from non-clinical or clinical data to suggest that DARZALEX has the potential to delay ventricular repolarization.

12.3 Pharmacokinetics

Daratumumab area under the concentration-time curve (AUC) increases more than proportionally over a dosage range from 1 to 24 mg/kg (0.06 to 1.5 times the approved recommended dosage) as monotherapy or 1 to 16 mg/kg (0.06 to 1 time the approved recommended dosage) as combination therapy.

Following administration of the approved recommended dosage of DARZALEX as monotherapy or in combination therapy, the mean serum maximal concentration (Cmax) was approximately 2.7 to 3-fold higher at the end of weekly dosing compared to the first dose. The mean ± standard deviation (SD) trough serum concentration (Cmin) at the end of weekly dosing was 573 ± 332 µg/mL when DARZALEX was administered as monotherapy and 502 ± 196 to 607 ± 231 µg/mL when DARZALEX was administered as combination therapy. Split dosing of the first dose resulted in a different PK profile in the first day compared to single dosing; however, similar Cmaxand Cminconcentrations were both predicted and observed following the administration of the second split dose on Week 1 Day 2.

When DARZALEX was administered as monotherapy, daratumumab steady state was achieved approximately 5 months into the every 4-week dosing period (by the 21st infusion). At steady state, daratumumab mean ± SD accumulation ratio for Cmax was 1.6 ± 0.5.

Distribution

Daratumumab volume of distribution was 4.7 ± 1.3 L as monotherapy and 4.4 ± 1.5 L as combination therapy following administration of the approved dosage.

Elimination

Daratumumab clearance decreased with increasing dose and with multiple dosing. The mean ± SD linear clearance was estimated to be 171.4 ± 95.3 mL/day and the mean ± SD estimated terminal half-life associated with linear clearance was 18 ± 9 days following administration of the approved recommended dosage of DARZALEX as monotherapy. Terminal half-life was similar when DARZALEX was administered as combination therapy.

Specific Populations

No clinically significant differences in the pharmacokinetics of daratumumab as monotherapy or as combination therapy were observed based on sex, age (31 to 93 years), mild [total bilirubin 1 to 1.5 times upper limit of normal (ULN) or aspartate aminotransaminase (AST)>ULN] and moderate (total bilirubin 1.5 to 3 times ULN and any AST) hepatic impairment, or renal impairment [Creatinine clearance (CLcr) 15–89 mL/min]. The effect of severe (total bilirubin >3 times ULN and any AST) hepatic impairment on daratumumab pharmacokinetics is unknown.

Body Weight

The central volume of distribution and clearance of daratumumab increased with increasing body weight.

12.6 Immunogenicity

The observed incidence of anti-drug antibody (ADA, including neutralizing antibody) is highly dependent on the sensitivity and specificity of the assay. Differences in assay methods preclude meaningful comparisons of the incidence of ADA in the studies described below with the incidence of ADA in other studies, including those of daratumumab or of other daratumumab products.

With the median DARZALEX treatment ranging from 3.3 to 48 months across 10 clinical trials of patients with multiple myeloma treated with DARZALEX as monotherapy or as combination therapies, the incidence of anti-daratumumab antibody development was 0.6% (14/2,179) and 12 patients tested positive for neutralizing antibodies. Because of the low occurrence of anti-drug antibodies, the effect of these antibodies on the pharmacokinetics, pharmacodynamics, safety, and/or effectiveness of daratumumab products is unknown.

13 NONCLINICAL TOXICOLOGY

13.1 Carcinogenesis, Mutagenesis, Impairment of Fertility

No carcinogenicity or genotoxicity studies have been conducted with daratumumab. No animal studies have been performed to evaluate the potential effects of daratumumab on reproduction or development, or to determine potential effects on fertility in males or females.

14 CLINICAL STUDIES

14.1 Newly Diagnosed Multiple Myeloma

Combination Treatment with Lenalidomide and Dexamethasone in Patients Ineligible for Autologous Stem Cell Transplant

MAIA (NCT02252172), an open-label, randomized, active-controlled trial, compared treatment with DARZALEX 16 mg/kg in combination with lenalidomide and low-dose dexamethasone (DRd) to treatment with lenalidomide and low-dose dexamethasone (Rd) in patients with newly diagnosed multiple myeloma ineligible for autologous stem cell transplant. Lenalidomide (25 mg once daily orally on Days 1–21 of repeated 28-day [4-week] cycles) was given with low dose oral or intravenous dexamethasone 40 mg/week (or a reduced dose of 20 mg/week for patients >75 years or body mass index [BMI] <18.5). On DARZALEX infusion days, the dexamethasone dose was given as a pre-infusion medication. Treatment was continued in both arms until disease progression or unacceptable toxicity.

A total of 737 patients were randomized: 368 to the DRd arm and 369 to the Rd arm. The baseline demographic and disease characteristics were similar between the two treatment groups. The median age was 73 (range: 45–90) years, with 44% of the patients ≥75 years of age. Fifty-two percent (52%) of patients were male, 92% White, 4% Black or African American, and 1% Asian. Three percent (3%) of patients reported an ethnicity of Hispanic or Latino. Thirty-four (34%) had an Eastern Cooperative Oncology Group (ECOG) performance score of 0, 50% had an ECOG performance score of 1 and 17% had an ECOG performance score of ≥2. Twenty-seven percent had International Staging System (ISS) Stage I, 43% had ISS Stage II and 29% had ISS Stage III disease. Efficacy was evaluated by progression free survival (PFS) based on International Myeloma Working Group (IMWG) criteria.

MAIA demonstrated an improvement in Progression Free Survival (PFS) in the DRd arm as compared to the Rd arm; the median PFS had not been reached in the DRd arm and was 31.9 months in the Rd arm (hazard ratio [HR]=0.56; 95% CI: 0.43, 0.73; p<0.0001), representing 44% reduction in the risk of disease progression or death in patients treated with DRd. After a median follow-up of 64 months, the median PFS was 61.9 months (95% CI: 54.8, NE) in the DRd arm and 34.4 months (95% CI: 29.6, 39.2) in the Rd arm.

Figure 1: Kaplan-Meier Curve of PFS in MAIA [PFS median follow-up of 28 months]

After a median follow-up of 56 months, MAIA demonstrated an improvement in overall survival (OS) in the DRd arm as compared to the Rd arm (HR=0.68; 95% CI: 0.53, 0.86; p=0.0013), representing a 32% reduction in the risk of death in patients treated in the DRd arm. Median OS had not been reached for either arm.

After a median follow-up of 89 months, the median OS was 90.3 months (95% CI: 80.8, NE) in the DRd arm and 64.1 months (95% CI: 56.0, 70.8) in the Rd arm.

Figure 2: Kaplan-Meier Curve of OS in MAIA [OS median follow-up of 56 months]

Additional efficacy results from MAIA are presented in Table 23.

Table 23: Additional Efficacy Results From MAIA [Based on intent-to-treat population.]
 | DRd (N=368) | Rd (N=369)
Overall response (sCR+CR+VGPR+PR) n(%) | 342 (92.9%) | 300 (81.3%)
p-value [p-value from Cochran Mantel-Haenszel Chi-Squared test.] | <0.0001
Stringent complete response (sCR) | 112 (30.4%) | 46 (12.5%)
Complete response (CR) | 63 (17.1%) | 46 (12.5%)
Very good partial response (VGPR) | 117 (31.8%) | 104 (28.2%)
Partial response (PR) | 50 (13.6%) | 104 (28.2%)
CR or better (sCR + CR) | 175 (47.6%) | 92 (24.9%)
p-value | <0.0001
VGPR or better (sCR + CR + VGPR) | 292 (79.3%) | 196 (53.1%)
p-value | <0.0001
MRD negativity rate , [Based on threshold of 10^-5 using a next-generation sequencing assay (clonoSEQ).] n(%) | 89 (24.2%) | 27 (7.3%)
95% CI (%) | (19.9%, 28.9%) | (4.9%, 10.5%)
p-value [p-value from Fisherʼs exact test.] | <0.0001
MRD negativity rate in patients with CR or better
Number of patients with CR or better | N=175 | N=92
MRD negativity rate n(%) | 89 (50.9%) | 27 (29.3%)
95% CI (%) | (43.2%, 58.5%) | (20.3%, 39.8%)
DRd=daratumumab-lenalidomide-dexamethasone; Rd=lenalidomide-dexamethasone; MRD=minimal residual disease; CI=confidence interval

In responders, the median time to response was 1.05 months (range: 0.2 to 12.1 months) in the DRd group and 1.05 months (range: 0.3 to 15.3 months) in the Rd group. The median duration of response had not been reached in the DRd group and was 34.7 months (95% CI: 30.8, not estimable) in the Rd group.

Combination Treatment with Bortezomib, Melphalan and Prednisone (VMP) in Patients Ineligible for Autologous Stem Cell Transplant

ALCYONE (NCT02195479), an open-label, randomized, active-controlled trial, compared treatment with DARZALEX 16 mg/kg in combination with bortezomib, melphalan and prednisone (D-VMP), to treatment with VMP in patients with newly diagnosed multiple myeloma ineligible for autologous stem cell transplant. Bortezomib was administered by subcutaneous (SC) injection at a dose of 1.3 mg/m^2 body surface area twice weekly at Weeks 1, 2, 4 and 5 for the first 6-week cycle (Cycle 1; 8 doses), followed by once weekly administrations at Weeks 1, 2, 4 and 5 for eight more 6-week cycles (Cycles 2–9; 4 doses per cycle). Melphalan at 9 mg/m^2, and prednisone at 60 mg/m^2 were orally administered on Days 1 to 4 of the nine 6-week cycles (Cycles 1–9). DARZALEX was continued until disease progression or unacceptable toxicity.

A total of 706 patients were randomized: 350 to the D-VMP arm and 356 to the VMP arm. The baseline demographic and disease characteristics were similar between the two treatment groups. The median age was 71 (range: 40–93) years, with 30% of the patients ≥75 years of age. The majority were white (85%), female (54%), 25% had an ECOG performance score of 0, 50% had an ECOG performance score of 1 and 25% had an ECOG performance score of 2. Nineteen percent of patients had ISS Stage I, 42% had ISS Stage II and 38% had ISS Stage III disease. Efficacy was evaluated by PFS based on IMWG criteria and overall survival (OS).

ALCYONE demonstrated an improvement in PFS in the D-VMP arm as compared to the VMP arm (HR=0.50; 95% CI: 0.38, 0.65; p<0.0001), representing a 50% reduction in the risk of disease progression or death in patients treated with D-VMP. After a median follow-up of 40 months, the median PFS was 36.4 months (95% CI: 32.1, 45.9) in the D-VMP arm and 19.3 months (95% CI: 18.0, 20.4) in the VMP arm.

Figure 3: Kaplan-Meier Curve of PFS in ALCYONE [PFS median follow-up of 16.5 months]

After a median follow-up of 40 months, ALCYONE demonstrated an improvement in overall survival (OS) in the D-VMP arm as compared to the VMP arm (HR=0.60; 95% CI: 0.46, 0.80; p=0.0003), representing a 40% reduction in the risk of death in patients treated in the D-VMP arm. Median OS had not been reached for either arm.

After a median follow-up of 87 months, the median OS was 83 months (95% CI: 72.5, NE) in the D-VMP arm and 53.6 months (95% CI: 46.3, 60.9) in the VMP arm.

Figure 4: Kaplan-Meier Curve of OS in ALCYONE [OS median follow-up of 40 months]

Additional efficacy results from ALCYONE are presented in Table 24.

Table 24: Additional Efficacy Results From ALCYONE
 | D-VMP (N=350) | VMP (N=356)
Overall response (sCR+CR+VGPR+PR) n(%) [Based on intent-to-treat population] | 318 (90.9%) | 263 (73.9%)
p-value [p-value from Cochran Mantel-Haenszel Chi-Squared test.] | <0.0001
Stringent complete response (sCR) | 63 (18.0%) | 25 (7.0%)
Complete response (CR) | 86 (24.6%) | 62 (17.4%)
Very good partial response (VGPR) | 100 (28.6%) | 90 (25.3%)
Partial response (PR) | 69 (19.7%) | 86 (24.2%)
MRD negativity rate , [Based on threshold of 10^-5 using a next-generation sequencing assay (clonoSEQ).] n(%) | 78 (22.3%) | 22 (6.2%)
95% CI (%) | (18.0, 27.0) | (3.9, 9.2)
p-value [p-value from Fisher's exact test.] | <0.0001
MRD negativity rate in patients with CR or better
Number of patients with CR or better | N=149 | N=87
MRD negativity rate n(%) | 74 (49.7%) | 22 (25.3%)
95% CI (%) | (41.4, 58.0) | (16.6, 35.7)
D-VMP = daratumumab-bortezomib-melphalan-prednisone; VMP = bortezomib-melphalan-prednisone; MRD = minimal residual disease; CI = confidence interval

In responders, the median time to response was 0.79 months (range: 0.4 to 15.5 months) in the D-VMP group and 0.82 months (range: 0.7 to 12.6 months) in the VMP group. The median duration of response had not been reached in the D-VMP group and was 21.3 months (range: 0.5+, 23.7+) in the VMP group.

Combination Treatment with Bortezomib, Thalidomide and Dexamethasone in Patients Eligible for Autologous Stem Cell Transplant (ASCT)

CASSIOPEIA (NCT02541383), an open-label, randomized, active-controlled trial compared induction and consolidation treatment with DARZALEX 16 mg/kg in combination with bortezomib, thalidomide and dexamethasone (DVTd) to treatment with bortezomib, thalidomide and dexamethasone (VTd) in patients with newly diagnosed multiple myeloma eligible for ASCT. The consolidation phase of treatment began a minimum of 30 days post-ASCT, when the patient had recovered sufficiently, and engraftment was complete. The trial was limited to patients 65 years of age and younger. Bortezomib was administered by subcutaneous (SC) injection or intravenous (IV) injection at a dose of 1.3 mg/m^2body surface area twice weekly for two weeks (Days 1, 4, 8, and 11) of repeated 28-day (4-week) induction treatment cycles (Cycles 1–4) and two consolidation cycles (Cycles 5 and 6) following ASCT after Cycle 4. Thalidomide was administered orally at 100 mg daily during the six bortezomib cycles. Dexamethasone (oral or intravenous) was administered at 40 mg on Days 1, 2, 8, 9, 15, 16, 22 and 23 of Cycles 1 and 2, and at 40 mg on Days 1–2 and 20 mg on subsequent dosing days (Days 8, 9, 15, 16) of Cycles 3–4. Dexamethasone 20 mg was administered on Days 1, 2, 8, 9, 15, 16 in Cycles 5 and 6. On the days of DARZALEX infusion, the dexamethasone dose was administered intravenously as a pre-infusion medication.

A total of 1,085 patients were randomized: 543 to the DVTd arm and 542 to the VTd arm. The baseline demographic and disease characteristics were similar between the two treatment groups. The median age was 58 years (range: 22 to 65 years). The majority were male (59%), 48% had an ECOG performance score of 0, 42% had an ECOG performance score of 1 and 10% had an ECOG performance score of 2. Forty percent had ISS Stage I, 45% had ISS Stage II and 15% had ISS Stage III disease.

Efficacy was evaluated by stringent Complete Response (sCR) rate at Day 100 post-transplant, Complete Response Rate (CR) at Day 100 post-transplant, and Progression-Free Survival (PFS).

Table 25: Efficacy Results From CASSIOPEIA at Day 100 Post-Transplant
 | DVTd (N=543) | VTd (N=542)
Overall response (sCR+CR+VGPR+PR) n(%) [Based on intent-to-treat population] | 503 (92.6%) | 487 (89.9%)
Stringent complete response (sCR) | 157 (28.9%) | 110 (20.3%)
p-value [p-value from Cochran Mantel-Haenszel Chi-Squared test.] | 0.0010
Complete response (CR) | 54 (9.9%) | 31 (5.7%)
Very good partial response (VGPR) | 242 (44.6%) | 282 (52.0%)
Partial response (PR) | 50 (9.2%) | 64 (11.8%)
D-VTd = daratumumab-bortezomib-thalidomide-dexamethasone; VTd = bortezomib-thalidomide-dexamethasone

CASSIOPEIA demonstrated an improvement in PFS in the DVTd arm as compared to the VTd arm; with a median follow up of 18.8 months, the median PFS had not been reached in either arm. Treatment with DVTd resulted in a reduction in the risk of progression or death by 53% compared to VTd alone (HR=0.47; 95% CI: 0.33, 0.67; p<0.0001).

Figure 5: Kaplan-Meier Curve of PFS in CASSIOPEIA [based on interim analysis and the boundary for PFS was crossed.]

14.2 Relapsed/Refractory Multiple Myeloma

Combination Treatment with Lenalidomide and Dexamethasone

POLLUX (NCT02076009), an open-label, randomized, active-controlled trial, compared treatment with DARZALEX 16 mg/kg in combination with lenalidomide and low-dose dexamethasone (DRd) to treatment with lenalidomide and low-dose dexamethasone (Rd) in patients with multiple myeloma who had received at least one prior therapy. Lenalidomide (25 mg once daily orally on Days 1–21 of repeated 28-day [4-week] cycles) was given with low dose oral or intravenous dexamethasone 40 mg/week (or a reduced dose of 20 mg/week for patients >75 years or BMI <18.5). On DARZALEX infusion days, 20 mg of the dexamethasone dose was given as a pre-infusion medication and the remainder given the day after the infusion. For patients on a reduced dexamethasone dose, the entire 20 mg dose was given as a DARZALEX pre-infusion medication. Dose adjustments for lenalidomide and dexamethasone were applied according to manufacturer's prescribing information. Treatment was continued in both arms until disease progression or unacceptable toxicity.

A total of 569 patients were randomized; 286 to the DRd arm and 283 to the Rd arm. The baseline demographic and disease characteristics were similar between the DARZALEX and the control arm. The median patient age was 65 years (range 34 to 89 years), 11% were ≥75 years, 59% were male; 69% White, 18% Asian, and 3% African American. Patients had received a median of 1 prior line of therapy. Sixty-three percent (63%) of patients had received prior autologous stem cell transplantation (ASCT). The majority of patients (86%) received a prior PI, 55% of patients had received a prior immunomodulatory agent, including 18% of patients who had received prior lenalidomide; and 44% of patients had received both a prior PI and immunomodulatory agent. At baseline, 27% of patients were refractory to the last line of treatment. Eighteen percent (18%) of patients were refractory to a PI only, and 21% were refractory to bortezomib. Efficacy was evaluated by PFS based on IMWG criteria.

POLLUX demonstrated an improvement in PFS in the DRd arm as compared to the Rd arm (HR=0.37; 95% CI: 0.27, 0.52; p<0.0001), representing a 63% reduction in the risk of disease progression or death in patients treated with DRd. After a median follow-up of 55 months, the median PFS was 45.0 months (95% CI: 34.1, 53.9) in the DRd arm and was 17.5 months (95% CI: 13.9, 20.8) in the Rd arm.

Figure 6: Kaplan-Meier Curve of PFS in POLLUX [PFS median follow-up of 13.5 months]

After a median follow-up of 80 months, POLLUX demonstrated an improvement in overall survival (OS) in the DRd arm as compared to the Rd arm (HR=0.73; 95% CI: 0.58, 0.91; p=0.0044), representing a 27% reduction in the risk of death in patients treated in the DRd arm. The median OS was 67.6 months in the DRd arm and 51.8 months in the Rd arm.

Figure 7: Kaplan-Meier Curve of OS in POLLUX

Additional efficacy results from POLLUX are presented in Table 26.

Table 26: Additional Efficacy Results From POLLUX [Based on Intent-to-treat population]
 | DRd (N=286) | Rd (N=283)
Overall response (sCR+CR+VGPR+PR) | 261 (91.3%) | 211 (74.6%)
p-value [p-value from Cochran Mantel-Haenszel Chi-Squared test.] | <0.0001
Stringent complete response (sCR) | 51 (17.8%) | 20 (7.1%)
Complete response (CR) | 70 (24.5%) | 33 (11.7%)
Very good partial response (VGPR) | 92 (32.2%) | 69 (24.4%)
Partial response (PR) | 48 (16.8%) | 89 (31.4%)
DRd = daratumumab- lenalidomide-dexamethasone; Rd = lenalidomide-dexamethasone

In responders, the median time to response was 1 month (range: 0.9 to 13 months) in the DRd group and 1.1 months (range: 0.9 to 10 months) in the Rd group. The median duration of response had not been reached in the DRd group (range: 1+ to 19.8+ months) and was 17.4 months (range: 1.4 to 18.5+ months) in the Rd group.

Combination Treatment with Bortezomib and Dexamethasone

CASTOR (NCT02136134), an open-label, randomized, active-controlled Phase 3 trial, compared treatment with DARZALEX 16 mg/kg in combination with bortezomib and dexamethasone (DVd), to treatment with bortezomib and dexamethasone (Vd) in patients with multiple myeloma who had received at least one prior therapy. Bortezomib was administered by SC injection or IV injection at a dose of 1.3 mg/m^2 body surface area twice weekly for two weeks (Days 1, 4, 8, and 11) of repeated 21 day (3-week) treatment cycles, for a total of 8 cycles. Dexamethasone was administered orally at a dose of 20 mg on Days 1, 2, 4, 5, 8, 9, 11, and 12 of each of the 8 bortezomib cycles (80 mg/week for two out of three weeks of the bortezomib cycle) or a reduced dose of 20 mg/week for patients >75 years, BMI <18.5, poorly controlled diabetes mellitus or prior intolerance to steroid therapy. On the days of DARZALEX infusion, 20 mg of the dexamethasone dose was administered as a pre-infusion medication. For patients on a reduced dexamethasone dose, the entire 20 mg dose was given as a DARZALEX pre-infusion medication. Bortezomib and dexamethasone were given for 8 three-week cycles in both treatment arms; whereas DARZALEX was given until disease progression. However, dexamethasone 20 mg was continued as a DARZALEX pre-infusion medication in the DVd arm. Dose adjustments for bortezomib and dexamethasone were applied according to manufacturer's prescribing information.

A total of 498 patients were randomized; 251 to the DVd arm and 247 to the Vd arm. The baseline demographic and disease characteristics were similar between the DARZALEX and the control arm. The median patient age was 64 years (range 30 to 88 years); 12% were ≥75 years, 57% were male; 87% White, 5% Asian and 4% African American. Patients had received a median of 2 prior lines of therapy and 61% of patients had received prior autologous stem cell transplantation (ASCT). Sixty-nine percent (69%) of patients had received a prior PI (66% received bortezomib) and 76% of patients received an immunomodulatory agent (42% received lenalidomide). At baseline, 32% of patients were refractory to the last line of treatment and the proportions of patients refractory to any specific prior therapy were in general well balanced between the treatment groups. Thirty-three percent (33%) of patients were refractory to an immunomodulatory agent only, with 24% patients in the DVd arm and 33% of patients in the Vd arm respectively refractory to lenalidomide. Efficacy was evaluated by PFS based on IMWG criteria.

CASTOR demonstrated an improvement in PFS in the DVd arm as compared to the Vd arm (HR=0.39; 95% CI: 0.28, 0.53; p<0.0001), representing a 61% reduction in the risk of disease progression or death for patients treated with DVd versus Vd. After a median follow-up of 50 months, the median PFS was 16.7 months (95% CI: 13.1, 19.4) in the DVd arm and was 7.1 months (95% CI: 6.2, 7.7) in the Vd arm.

Figure 8: Kaplan-Meier Curve of PFS in CASTOR [PFS median follow-up of 7.4 months]

After a median follow-up of 73 months, CASTOR demonstrated an improvement in overall survival (OS) in the DVd arm as compared to the Vd arm (HR=0.74; 95% CI: 0.59, 0.92; p=0.0075), representing a 26% reduction in the risk of death in patients treated in the DVd arm. The median OS was 49.6 months in the DVd arm and 38.5 months in the Vd arm.

Figure 9: Kaplan-Meier Curve of OS in CASTOR

Additional efficacy results from CASTOR are presented in Table 27.

Table 27: Additional Efficacy Results From CASTOR [Based on Intent-to-treat population]
 | DVd (N=251) | Vd (N=247)
Overall response (sCR+CR+VGPR+PR) | 199 (79.3%) | 148 (59.9%)
P-value [p-value from Cochran Mantel-Haenszel Chi-Squared test.] | <0.0001
Stringent complete response (sCR) | 11 (4.4%) | 5 (2.0%)
Complete response (CR) | 35 (13.9%) | 16 (6.5%)
Very good partial response (VGPR) | 96 (38.2%) | 47 (19.0%)
Partial response (PR) | 57 (22.7%) | 80 (32.4%)
DVd = daratumumab- bortezomib-dexamethasone; Vd = bortezomib-dexamethasone

In responders, the median time to response was 0.8 months (range: 0.7 to 4 months) in the DVd group and 1.5 months (range: 0.7 to 5 months) in the Vd group. The median duration of response had not been reached in the DVd group (range: 1.4+ to 14.1+ months) and was 7.9 months (1.4+ to 12+ months) in the Vd group.

Combination Treatment with Twice-Weekly (20/56 mg/m^2) Carfilzomib and Dexamethasone

CANDOR (NCT03158688) was a randomized, open-label, multicenter trial which evaluated the combination of DARZALEX with twice-weekly carfilzomib and dexamethasone (DKd) versus twice-weekly carfilzomib and dexamethasone (Kd) in patients with relapsed or refractory multiple myeloma who had received at least 1 to 3 prior lines of therapy. Patients who had the following were excluded from the trial: known moderate or severe persistent asthma within the past 2 years, known chronic obstructive pulmonary disease (COPD) with a FEV1 <50% of predicted normal, and active congestive heart failure. Randomization was stratified by the ISS (stage 1 or 2 vs stage 3) at screening, prior proteasome inhibitor exposure (yes vs no), number of prior lines of therapy (1 vs ≥2), or prior cluster differentiation antigen 38 (CD38) antibody therapy (yes vs no).

DARZALEX was administered intravenously at a dose of 8 mg/kg in Cycle 1 on Days 1 and 2. Thereafter, DARZALEX was administered intravenously at a dose of 16 mg/kg on Days 8, 15 and 22 of Cycle 1; Days 1, 8 and 15 and 22 of Cycle 2; Days 1 and 15 of Cycles 3 to 6; and Day 1 of each 28-day cycle until disease progression. Carfilzomib was administered intravenously at a dose of 20 mg/m^2in Cycle 1 on Days 1 and 2; at a dose of 56 mg/m^2 in Cycle 1 on Days 8, 9, 15, and 16 ; and at a dose 56 mg/m^2 on Days 1, 2, 8, 9, 15, and 16 of each 28-day cycle thereafter. Dexamethasone 20 mg was administered orally or intravenously on Days 1, 2, 8, 9, 15 and 16 and then 40 mg orally or intravenously on Day 22 of each 28-day cycle. For patients >75 years on a reduced dexamethasone dose of 20 mg, the entire 20 mg dose was given as a DARZALEX pre-infusion medication on days when DARZALEX was administered. Dosing of dexamethasone was otherwise split across days when carfilzomib was administered in both study arms. Treatment was continued in both arms until disease progression or unacceptable toxicity.

A total of 466 patients were randomized; 312 to the DKd arm and 154 to the Kd arm. The baseline demographic and disease characteristics were similar between arms. The median age was 64 years (range 29 to 84 years), 9% were ≥75 years, 58% were male; 79% White, 14% Asian, and 2% Black. Patients had received a median of 2 prior lines of therapy and 58% of patients had received prior autologous stem cell transplantation (ASCT). The majority of patients (92%) received a prior PI and of those 34% were refractory to PI including regimen. Fourty-two percent (42%) of patients had received prior lenalidomide and of those, 33% were refractory to a lenalidomide containing regimen.

Efficacy was evaluated by IRC evaluation of PFS based on the IMWG response criteria. Efficacy results are provided in Figure 10. CANDOR demonstrated an improvement in PFS in the DKd arm as compared to the Kd arm; the median PFS had not been reached in the DKd arm and was 15.8 months in the Kd arm (hazard ratio [HR]=0.63; 95% CI: 0.46, 0.85; p=0.0014), representing 37% reduction in the risk of disease progression or death for patients treated with DKd versus Kd.

Figure 10: Kaplan-Meier Curve of PFS in CANDOR

Additional efficacy results from CANDOR are presented in Table 28.

Table 28: Additional Efficacy Results From CANDOR (Intent-to-Treat Population)
 | DKd (N=312) | Kd (N=154)
Overall response (sCR+CR+VGPR+PR) n(%) | 263 (84%) | 115 (75%)
95% CI (%) | (80, 88) | (67, 81)
p-value [p-value from the stratified Cochran Mantel-Haenszel Chi-Squared test] (1-sided) | 0.0040
Complete response (CR) | 89 (28%) | 16 (10%)
Very good partial response (VGPR) | 127 (41%) | 59 (38%)
Partial response (PR) | 47 (15%) | 40 (26%)
MRD [-] CR rate at 12 months n(%) [MRD[-]CR (at a 10^-5 level) is defined as achievement of CR per IMWG-URC and MRD[-] status as assessed by the next-generation sequencing assay (ClonoSEQ).] | 39 (12%) | 2 (1.3%)
95% CI (%) | (9, 17) | (0.2, 4.6)
p-value (1-sided) | <0.0001
MRD [-] CR | 43 (14%) | 5 (3.2%)
DKd = daratumumab-carfilzomib-dexamethasone; Kd =carfilzomib-dexamethasone; MRD [-] CR=minimal residual disease; CI=confidence interval

The median time to response was 1 month (range: 1 to 14 months) in the DKd group and 1 month (range: 1 to 10 months) in the Kd group. The median duration of response had not been reached in the DKd group and was 16.6 months (95% CI: 13.9, not estimable) in the Kd group.

Combination Treatment with Once-Weekly (20/70 mg/m^2) Carfilzomib and Dexamethasone

EQUULEUS (NCT01998971) was an open-label, multi-cohort trial which evaluated the combination of DARZALEX with one-weekly carfilzomib and dexamethasone in patients with relapsed or refractory multiple myeloma who had received at least 1 to 3 prior lines of therapy. Patients who had the following were excluded from the trial: known moderate or severe persistent asthma within the past 2 years, known chronic obstructive pulmonary disease (COPD) with a FEV1 <50% of predicted normal, or active congestive heart failure (defined as New York Heart Association Class III–IV).

Ten patients were administered DARZALEX at a dose of 16 mg/kg intravenously on Cycle 1, Day 1 and the remaining patients were administered DARZALEX at a dose of 8 mg/kg intravenously on Cycle 1, Days 1 and 2. Thereafter, DARZALEX was administered intravenously at a dose of 16 mg/kg on Days 8, 15 and 22 of Cycle 1; Days 1, 8, 15 and 22 of Cycle 2; Days 1 and 15 of Cycles 3 to 6; and then Day 1 for the remaining cycles of each 28 day cycle. Carfilzomib was administered intravenously once weekly at a dose of 20 mg/m^2 on Cycle 1 Day 1 and escalated to dose of 70 mg/m^2 on Cycle 1 Days 8 and 15, and Days 1, 8, and 15 of each subsequent 28-day cycle. In Cycles 1 and 2, dexamethasone 20 mg was administered orally or intravenously on Days 1, 2, 8, 9, 15, 16, 22 and 23; in cycles 3 to 6, dexamethasone 20 mg was administered orally or intravenously on Days 1, 2, 15 and 16 and at a dose of 40 mg on Day 8 and 22; and in cycles 7 and thereafter, dexamethasone 20 mg was administered orally or intravenously on Days 1 and 2 and at a dose of 40 mg on Days 8, 15, and 22. For patients >75 years of age, dexamethasone 20 mg was administered orally or intravenously weekly after the first week. Treatment continued until disease progression or unacceptable toxicity.

The EQUULEUS trial enrolled 85 patients. The median patient age was 66 years (range: 38 to 85 years) with 9% of patients ≥75 years of age; 54% were male; 80% were White, 3.5% were Black and 3.5% were Asian. Patients in the study had received a median of 2 prior lines of therapy. Seventy-three percent (73%) of patients had received prior ASCT. All patients received prior bortezomib, and 95% of patients received prior lenalidomide. Fifty-nine percent (59%) of patients were refractory to lenalidomide and 29% of patients were refractory to both a PI an IMiD.

Efficacy results were based on overall response rate using IMWG criteria. Efficacy results are provided in Table 29. The median time to response was 0.95 months (range: 0.9, 14.3). The median duration of response was 28 months (95% CI: 20.5, not estimable).

Table 29: Efficacy results for EQUULEUS
 | N=85
Overall response rate (ORR) | 69 (81%)
95% CI (%) | (71, 89)
Stringent complete response (sCR) | 18 (21%)
Complete response (CR) | 12 (14%)
Very good partial response (VGPR) | 28 (33%)
Partial response (PR) | 11 (13%)
ORR = sCR+CR+VGPR+PR
CI = confidence interval

Combination Treatment with Pomalidomide and Dexamethasone

EQUULEUS (NCT01998971) was an open-label trial in which 103 patients with multiple myeloma who had received a prior PI and an immunomodulatory agent, received 16 mg/kg DARZALEX in combination with pomalidomide and low-dose dexamethasone until disease progression. Pomalidomide (4 mg once daily orally on Days 1–21 of repeated 28-day [4-week] cycles) was given with low dose oral or intravenous dexamethasone 40 mg/week (reduced dose of 20 mg/week for patients >75 years or BMI <18.5). On DARZALEX infusion days, 20 mg of the dexamethasone dose was given as a pre-infusion medication and the remainder given the day after the infusion. For patients on a reduced dexamethasone dose, the entire 20 mg dose was given as a DARZALEX pre-infusion medication.

The median patient age was 64 years (range: 35 to 86 years) with 8% of patients ≥75 years of age. Patients in the study had received a median of 4 prior lines of therapy. Seventy-four percent (74%) of patients had received prior ASCT. Ninety-eight percent (98%) of patients received prior bortezomib treatment, and 33% of patients received prior carfilzomib. All patients received prior lenalidomide treatment, with 98% of patients previously treated with the combination of bortezomib and lenalidomide. Eighty nine percent (89%) of patients were refractory to lenalidomide and 71% refractory to bortezomib; 64% of patients were refractory to bortezomib and lenalidomide.

Efficacy results were based on overall response rate as determined by Independent Review Committee using IMWG criteria (see Table 30).

Table 30: Efficacy Results for EQUULEUS
 | N=103
Overall response rate (ORR) | 61 (59.2%)
95% CI (%) | (49.1, 68.8)
Stringent complete response (sCR) | 8 (7.8%)
Complete response (CR) | 6 (5.8%)
Very good partial response (VGPR) | 29 (28.2%)
Partial response (PR) | 18 (17.5%)
ORR = sCR+CR+VGPR+PR
CI = Confidence Interval

The median time to response was 1 month (range: 0.9 to 2.8 months). The median duration of response was 13.6 months (range: 0.9+ to 14.6+ months).

Monotherapy

SIRIUS (NCT01985126), was an open-label trial evaluating DARZALEX monotherapy in patients with relapsed or refractory multiple myeloma who had received at least 3 prior lines of therapy including a proteasome inhibitor and an immunomodulatory agent or who were double-refractory to a proteasome inhibitor and an immunomodulatory agent. In 106 patients, DARZALEX 16 mg/kg was administered with pre- and post-infusion medication. Treatment continued until unacceptable toxicity or disease progression.

The median patient age was 63.5 years (range: 31 to 84 years), 49% were male and 79% were White. Patients had received a median of 5 prior lines of therapy. Eighty percent of patients had received prior autologous stem cell transplantation (ASCT). Prior therapies included bortezomib (99%), lenalidomide (99%), pomalidomide (63%) and carfilzomib (50%). At baseline, 97% of patients were refractory to the last line of treatment, 95% were refractory to both, a proteasome inhibitor (PI) and immunomodulatory agent, and 77% were refractory to alkylating agents.

Efficacy results were based on overall response rate as determined by the Independent Review Committee assessment using IMWG criteria (see Table 31).

Table 31: Efficacy Results for SIRIUS
 | N=106
Overall response rate (ORR) | 31 (29.2%)
95% CI (%) | (20.8, 38.9)
Stringent complete response (sCR) | 3 (2.8%)
Complete response (CR) | 0
Very good partial response (VGPR) | 10 (9.4%)
Partial response (PR) | 18 (17.0%)
ORR = sCR+CR+VGPR+PR
CI = confidence interval

The median time to response was 1 month (range: 0.9 to 5.6 months). The median duration of response was 7.4 months (range: 1.2 to 13.1+ months).

Study GEN501 (NCT00574288) was an open-label dose escalation trial evaluating DARZALEX monotherapy in patients with relapsed or refractory multiple myeloma who had received at least 2 different cytoreductive therapies. In 42 patients, DARZALEX 16 mg/kg was administered with pre- and post-infusion medication. Treatment continued until unacceptable toxicity or disease progression.

The median patient age was 64 years (range: 44 to 76 years), 64% were male and 76% were White. Patients in the study had received a median of 4 prior lines of therapy. Seventy-four percent of patients had received prior ASCT. Prior therapies included bortezomib (100%), lenalidomide (95%), pomalidomide (36%) and carfilzomib (19%). At baseline, 76% of patients were refractory to the last line of treatment, 64% of patients were refractory to both, a PI and an immunomodulatory agent, and 60% of patients were refractory to alkylating agents.

Overall response rate was 36% (95% CI: 21.6, 52.0%) with 1 CR and 3 VGPR. The median time to response was 1 month (range: 0.5 to 3.2 months). The median duration of response was not estimable (range: 2.2 to 13.1+ months).

15 REFERENCES

1. Chapuy, CI, RT Nicholson, MD Aguad, et al., 2015, Resolving the daratumumab interference with blood compatibility testing, Transfusion, 55:1545–1554 (accessible at http://onlinelibrary.wiley.com/doi/10.1111/trf.13069/epdf).

16 HOW SUPPLIED/STORAGE AND HANDLING

How Supplied

DARZALEX®(daratumumab) injection is a colorless to pale yellow, preservative-free solution for intravenous infusion.

NDC 57894-502-05 and NDC 57894-505-05 each contain one 100 mg/5 mL (20 mg/mL) single-dose vial

NDC 57894-502-20 and NDC 57894-505-20 each contain one 400 mg/20 mL (20 mg/mL) single-dose vial

Storage and Stability

Store in a refrigerator at 2°C to 8°C (36°F to 46°F).

Do not freeze or shake. Protect from light. This product contains no preservative.

17 PATIENT COUNSELING INFORMATION

Advise the patient to read the FDA-approved patient labeling (Patient Information).

Infusion-Related Reactions

Advise patients to seek immediate medical attention for any of the following signs and symptoms of infusion-related reactions: itchy, runny or blocked nose; fever, chills, nausea, vomiting, throat irritation, cough, headache, dizziness or lightheadedness, tachycardia, chest discomfort, wheezing, shortness of breath or difficulty breathing, itching, and blurred vision [see Warnings and Precautions (5.1)] .

Neutropenia

Advise patients to contact their healthcare provider if they have a fever [see Warnings and Precautions (5.3)] .

Thrombocytopenia

Advise patients to contact their healthcare provider if they notice signs of bruising or bleeding [see Warnings and Precautions (5.4)] .

Interference with Laboratory Tests

Advise patients to inform their healthcare providers, including personnel at blood transfusion centers that they are taking DARZALEX, in the event of a planned transfusion [see Warnings and Precautions (5.2)] .

Advise patients that DARZALEX can affect the results of some tests used to determine complete response in some patients and additional tests may be needed to evaluate response [see Warnings and Precautions (5.5)] .

Hepatitis B Virus (HBV) Reactivation

Advise patients to inform healthcare providers if they have ever had or might have a hepatitis B infection and that DARZALEX could cause hepatitis B virus to become active again [see Adverse Reactions (6.1)] .

Embryo-Fetal Toxicity

Advise pregnant women of the potential hazard to a fetus. Advise females of reproductive potential to inform their healthcare provider of a known or suspected pregnancy [see Warnings and Precautions (5.6), Use in Specific Populations (8.1, 8.3)] .

Advise females of reproductive potential to avoid becoming pregnant during treatment with DARZALEX and for 3 months after the last dose [see Use in Specific Populations (8.1, 8.3)] .

Advise patients that lenalidomide, pomalidomide, or thalidomide has the potential to cause fetal harm and has specific requirements regarding contraception, pregnancy testing, blood and sperm donation, and transmission in sperm. Lenalidomide, pomalidomide, and thalidomide are only available through a REMS program [see Use in Specific Populations (8.1, 8.3)] .

Hereditary Fructose Intolerance (HFI)

DARZALEX contains sorbitol. Advise patients with HFI of the risks related to sorbitol [see Description (11)] .

Manufactured by:
Janssen Biotech, Inc.
Horsham, PA 19044, USA
U.S. License Number 1864

For patent information: www.janssenpatents.com

© 2015–2021 Janssen Pharmaceutical Companies

PATIENT INFORMATION
DARZALEX®(Dar'-zah-lex)
(daratumumab)
injection, for intravenous use

DARZALEX may be used with other medicines called lenalidomide, thalidomide or pomalidomide. You should also read the Medication Guide that comes with lenalidomide, thalidomide or pomalidomide if you use DARZALEX with these medicines.

What is DARZALEX?
DARZALEX is a prescription medicine used to treat adults with multiple myeloma:

- in combination with the medicines lenalidomide and dexamethasone in people with newly diagnosed multiple myeloma who cannot receive a type of stem cell transplant that uses their own stem cells (autologous stem cell transplant) and in people whose multiple myeloma has come back or did not respond to treatment who have received at least one prior medicine to treat multiple myeloma.
- in combination with the medicines bortezomib, melphalan and prednisone, in people with newly diagnosed multiple myeloma who cannot receive a type of stem cell transplant that uses their own stem cells (autologous stem cell transplant).
- in combination with the medicines bortezomib, thalidomide, and dexamethasone in newly diagnosed people who are eligible to receive a type of stem cell transplant that uses their own stem cells (autologous stem cell transplant).
- in combination with the medicines bortezomib and dexamethasone, in people who have received at least one prior medicine to treat multiple myeloma.
- in combination with the medicines carfilzomib and dexamethasone, in people whose multiple myeloma has come back or did not respond to treatment who have received one to three prior medicines to treat multiple myeloma.
- in combination with the medicines pomalidomide and dexamethasone in people who have received at least two prior medicines to treat multiple myeloma, including lenalidomide and a proteasome inhibitor.
- alone in people who have received at least three prior medicines, including a proteasome inhibitor and an immunomodulatory agent, or did not respond to a proteasome inhibitor and an immunomodulatory agent.

It is not known if DARZALEX is safe and effective in children.

Do not receive DARZALEX:

if you have a history of a severe allergic reaction to daratumumab or any of the ingredients in DARZALEX. See the end of this leaflet for a complete list of ingredients in DARZALEX.

Before you receive DARZALEX, tell your healthcare provider about all of your medical conditions, including if you:

- have a history of breathing problems.
- have had shingles (herpes zoster).
- have ever had or might now have a hepatitis B infection as DARZALEX could cause hepatitis B virus to become active again. Your healthcare provider will check you for signs of this infection before, during and for some time after treatment with DARZALEX. Tell your healthcare provider right away if you get worsening tiredness or yellowing of your skin or white part of your eyes.
- have hereditary fructose intolerance (HFI). DARZALEX contains sorbitol. Sorbitol is a source of fructose. People with HFI cannot break down fructose, which may cause serious side effects.
- are pregnant or plan to become pregnant. DARZALEX may harm your unborn baby. Tell your healthcare provider right away if you become pregnant or think that you may be pregnant during treatment with DARZALEX.
  - Females who are able to become pregnant should use an effective method of birth control (contraception) during treatment and for 3 months after your last dose of DARZALEX. Talk to your healthcare provider about birth control methods that you can use during this time.
  - Before starting DARZALEX in combination with lenalidomide, pomalidomide, or thalidomide, females and males must agree to the instructions in the lenalidomide, pomalidomide, or thalidomide REMS program.
    - The lenalidomide, pomalidomide, and thalidomide REMS has more information about effective methods of birth control, pregnancy testing, and blood donation for females who can become pregnant.
    - For males who have female partners who can become pregnant, there is information in the lenalidomide, pomalidomide, and thalidomide REMS about sperm donation and how lenalidomide, pomalidomide, and thalidomide can pass into human semen.
- are breastfeeding or plan to breastfeed. It is not known if DARZALEX passes into your breast milk. You should not breastfeed during treatment with DARZALEX. Talk to your healthcare provider about the best way to feed your baby during treatment with DARZALEX.

Tell your healthcare provider about all the medicines you take, including prescription and over-the-counter medicines, vitamins, and herbal supplements.

How will I receive DARZALEX?

- DARZALEX may be given alone or together with other medicines used to treat multiple myeloma.
- DARZALEX will be given to you by your healthcare provider by intravenous (IV) infusion into your vein.
- Your healthcare provider will decide the time between doses as well as how many treatments you will receive.
- Your healthcare provider will give you medicines before each dose of DARZALEX and after each dose of DARZALEX to help reduce the risk of infusion-related reactions.
  If you miss any appointments, call your healthcare provider as soon as possible to reschedule your appointment.

What are the possible side effects of DARZALEX?
DARZALEX may cause serious reactions, including:

- Infusion-related reactions. Infusion-related reactions are common with DARZALEX. Serious allergic reactions and reactions due to release of certain substances by your body (systemic) that can lead to death, can happen with DARZALEX . Your healthcare provider may temporarily stop your infusion or completely stop treatment with DARZALEX if you have infusion-related reactions. Get medical help right away if you get any of the following symptoms:

- shortness of breath or trouble breathing
- dizziness or lightheadedness (hypotension)
- cough
- wheezing
- heart beating faster than usual
- low oxygen in the blood (hypoxia)

- throat tightness or irritation
- runny or stuffy nose
- headache
- itching
- high blood pressure
- eye pain

- nausea
- vomiting
- chills
- fever
- chest discomfort
- blurred vision

- Changes in blood tests. DARZALEX can affect the results of blood tests to match your blood type. These changes can last for up to 6 months after your final dose of DARZALEX. Your healthcare provider will do blood tests to match your blood type before you start treatment with DARZALEX. Tell all of your healthcare providers that you are being treated with DARZALEX before receiving blood transfusions.
- Decreases in blood cell counts. DARZALEX can decrease white blood cell counts which help fight infections and blood cells called platelets which help to clot blood. Decreases in blood cell counts are common with DARZALEX, but can be severe. Your healthcare provider will check your blood cell counts during treatment with DARZALEX. Tell your healthcare provider if you develop fever or have signs of bruising or bleeding.

The most common side effects of DARZALEX include:

- cold-like symptoms (upper respiratory infection)
- diarrhea
- constipation
- decreased red blood cells

- nerve damage causing tingling, numbness or pain
- tiredness
- swollen hands, ankles, or feet
- nausea

- cough
- fever
- shortness of breath
- feeling weak

These are not all the possible side effects of DARZALEX.
Call your doctor for medical advice about side effects. You may report side effects to FDA at 1-800-FDA-1088.

General information about the safe and effective use of DARZALEX.
Medicines are sometimes prescribed for purposes other than those listed in a Patient Information leaflet. You can ask your pharmacist or healthcare provider for information about DARZALEX that is written for health professionals.

What are the ingredients in DARZALEX?
Active ingredient: daratumumab
Inactive ingredients: may include glacial acetic acid, L-histidine, L-histidine hydrochloride monohydrate, L-methionine, mannitol, polysorbate 20, sodium acetate trihydrate, sodium chloride, sorbitol, and water for injection.
Manufactured by: Janssen Biotech, Inc., Horsham, PA 19044, USA; U.S. License Number 1864
For patent information: www.janssenpatents.com
© 2015–2021 Janssen Pharmaceutical Companies
For more information, call 1-800-526-7736 or go to www.DARZALEX.com.

This Patient Information has been approved by the U.S. Food and Drug Administration.

Revised: 11/2022

PRINCIPAL DISPLAY PANEL - 100 mg/5 mL Vial Carton

NDC 57894-502-05

DARZALEX®
(daratumumab)
Injection
100 mg/5 mL
(20 mg/mL)

For Intravenous Infusion Only
Dilute Before Use
Rx only
Single-dose vial.
Discard Unused Portion

janssen

PRINCIPAL DISPLAY PANEL - 100 mg/5 mL Vial Carton - 57894-505

NDC 57894-505-05

DARZALEX®
(daratumumab)
Injection
100 mg/5 mL
(20 mg/mL)

For Intravenous Infusion Only
Dilute Before Use
Rx only
One 5 mL Vial
Single-dose vial.
Discard unused portion.

janssen